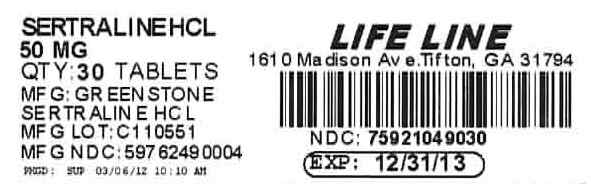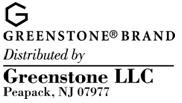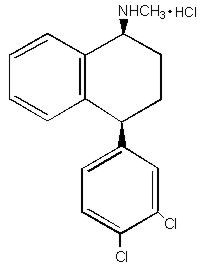 DRUG LABEL: SERTRALINE HYDROCHLORIDE
NDC: 75921-490 | Form: TABLET, FILM COATED
Manufacturer: Life Line Home Care Services
Category: prescription | Type: HUMAN PRESCRIPTION DRUG LABEL
Date: 20120306

ACTIVE INGREDIENTS: sertraline hydrochloride 50 mg/1 1
INACTIVE INGREDIENTS: dibasic calcium phosphate dihydrate; FD&C BLUE NO. 2; aluminum oxide; hydroxypropyl cellulose; HYPROMELLOSES; magnesium stearate; cellulose, microcrystalline; polyethylene glycol; polysorbate 80; titanium dioxide

SERTRALINE HYDROCHLORIDE
Tablets and Oral Concentrate

BOXED WARNING

Suicidality and Antidepressant Drugs

Antidepressants increased the risk compared to placebo of suicidal thinking and behavior (suicidality) in children, adolescents, and young adults in short-term studies of major depressive disorder (MDD) and other psychiatric disorders. Anyone considering the use of sertraline hydrochloride or any other antidepressant in a child, adolescent, or young adult must balance this risk with the clinical need. Short-term studies did not show an increase in the risk of suicidality with antidepressants compared to placebo in adults beyond age 24; there was a reduction in risk with antidepressants compared to placebo in adults aged 65 and older. Depression and certain other psychiatric disorders are themselves associated with increases in the risk of suicide. Patients of all ages who are started on antidepressant therapy should be monitored appropriately and observed closely for clinical worsening, suicidality, or unusual changes in behavior. Families and caregivers should be advised of the need for close observation and communication with the prescriber. Sertraline hydrochloride is not approved for use in pediatric patients except for patients with obsessive compulsive disorder (OCD). (See Warnings: Clinical Worsening and Suicide Risk, Precautions: Information for Patients, and Precautions: Pediatric Use)

DESCRIPTION

Sertraline hydrochloride is a selective serotonin reuptake inhibitor (SSRI) for oral administration. It has a molecular weight of 342.7. Sertraline hydrochloride has the following chemical name: (1S-cis)-4-(3,4-dichlorophenyl)-1,2,3,4-tetrahydro-N-methyl-1-naphthalenamine hydrochloride. The empirical formula C17H17NCl2•HCl is represented by the following structural formula:
Sertraline hydrochloride is a white crystalline powder that is slightly soluble in water and isopropyl alcohol, and sparingly soluble in ethanol.
Sertraline hydrochloride is supplied for oral administration as scored tablets equivalent to 25, 50 and 100 mg of sertraline and the following inactive ingredients: dibasic calcium phosphate dihydrate, D & C Yellow #10 aluminum lake (in 25 mg tablet), FD & C Blue #1 aluminum lake (in 25 mg tablet), FD & C Red #40 aluminum lake (in 25 mg tablet), FD & C Blue #2 aluminum lake (in 50 mg tablet), hydroxypropyl cellulose, hypromellose, magnesium stearate, microcrystalline cellulose, polyethylene glycol, polysorbate 80, sodium starch glycolate, synthetic yellow iron oxide (in 100 mg tablet), and titanium dioxide.
Sertraline hydrochloride oral concentrate is available in a multidose 60 mL bottle. Each mL of solution contains sertraline hydrochloride equivalent to 20 mg of sertraline. The solution contains the following inactive ingredients: glycerin, alcohol (12%), menthol, butylated hydroxytoluene (BHT). The oral concentrate must be diluted prior to administration (see PRECAUTIONS, Information for Patients and DOSAGE AND ADMINISTRATION.

CLINICAL PHARMACOLOGY

Pharmacodynamics

The mechanism of action of sertraline is presumed to be linked to its inhibition of CNS neuronal uptake of serotonin (5HT). Studies at clinically relevant doses in man have demonstrated that sertraline blocks the uptake of serotonin into human platelets. In vitro studies in animals also suggest that sertraline is a potent and selective inhibitor of neuronal serotonin reuptake and has only very weak effects on norepinephrine and dopamine neuronal reuptake. In vitro studies have shown that sertraline has no significant affinity for adrenergic (alpha1, alpha2, beta), cholinergic, GABA, dopaminergic, histaminergic, serotonergic (5HT1A, 5HT1B, 5HT2), or benzodiazepine receptors; antagonism of such receptors has been hypothesized to be associated with various anticholinergic, sedative, and cardiovascular effects for other psychotropic drugs. The chronic administration of sertraline was found in animals to down regulate brain norepinephrine receptors, as has been observed with other drugs effective in the treatment of major depressive disorder. Sertraline does not inhibit monoamine oxidase.

Pharmacokinetics

Systemic Bioavailability

In man, following oral once-daily dosing over the range of 50 to 200 mg for 14 days, mean peak plasma concentrations (Cmax) of sertraline occurred between 4.5 to 8.4 hours post-dosing. The average terminal elimination half-life of plasma sertraline is about 26 hours. Based on this pharmacokinetic parameter, steady-state sertraline plasma levels should be achieved after approximately one week of once-daily dosing. Linear dose-proportional pharmacokinetics were demonstrated in a single dose study in which the Cmax and area under the plasma concentration time curve (AUC) of sertraline were proportional to dose over a range of 50 to 200 mg. Consistent with the terminal elimination half-life, there is an approximately two-fold accumulation, compared to a single dose, of sertraline with repeated dosing over a 50 to 200 mg dose range. The single dose bioavailability of sertraline tablets is approximately equal to an equivalent dose of solution.

In a relative bioavailability study comparing the pharmacokinetics of 100 mg sertraline as the oral solution to a 100 mg sertraline tablet in 16 healthy adults, the solution to tablet ratio of geometric mean AUC and Cmax values were 114.8% and 120.6%, respectively. 90% confidence intervals (CI) were within the range of 80–125% with the exception of the upper 90% CI limit for Cmax which was 126.5%.

The effects of food on the bioavailability of the sertraline tablet and oral concentrate were studied in subjects administered a single dose with and without food. For the tablet, AUC was slightly increased when drug was administered with food but the Cmax was 25% greater, while the time to reach peak plasma concentration (Tmax) decreased from 8 hours post-dosing to 5.5 hours. For the oral concentrate, Tmax was slightly prolonged from 5.9 hours to 7.0 hours with food.

Metabolism

Sertraline undergoes extensive first pass metabolism. The principal initial pathway of metabolism for sertraline is N-demethylation. N-desmethylsertraline has a plasma terminal elimination half-life of 62 to 104 hours. Both in vitro biochemical and in vivo pharmacological testing have shown N-desmethylsertraline to be substantially less active than sertraline. Both sertraline and N-desmethylsertraline undergo oxidative deamination and subsequent reduction, hydroxylation, and glucuronide conjugation. In a study of radiolabeled sertraline involving two healthy male subjects, sertraline accounted for less than 5% of the plasma radioactivity. About 40–45% of the administered radioactivity was recovered in urine in 9 days. Unchanged sertraline was not detectable in the urine. For the same period, about 40–45% of the administered radioactivity was accounted for in feces, including 12–14% unchanged sertraline.

Desmethylsertraline exhibits time-related, dose dependent increases in AUC (0–24 hour), Cmax and Cmin, with about a 5–9 fold increase in these pharmacokinetic parameters between day 1 and day 14.

Protein Binding

In vitro protein binding studies performed with radiolabeled ^3H-sertraline showed that sertraline is highly bound to serum proteins (98%) in the range of 20 to 500 ng/mL. However, at up to 300 and 200 ng/mL concentrations, respectively, sertraline and N-desmethylsertraline did not alter the plasma protein binding of two other highly protein bound drugs, viz., warfarin and propranolol (see PRECAUTIONS).

Pediatric Pharmacokinetics

Sertraline pharmacokinetics were evaluated in a group of 61 pediatric patients (29 aged 6–12 years, 32 aged 13–17 years) with a DSM-III-R diagnosis of major depressive disorder or obsessive-compulsive disorder. Patients included both males (N=28) and females (N=33). During 42 days of chronic sertraline dosing, sertraline was titrated up to 200 mg/day and maintained at that dose for a minimum of 11 days. On the final day of sertraline 200 mg/day, the 6–12 year old group exhibited a mean sertraline AUC (0–24 hr) of 3107 ng-hr/mL, mean Cmax of 165 ng/mL, and mean half-life of 26.2 hr. The 13–17 year old group exhibited a mean sertraline AUC (0–24 hr) of 2296 ng-hr/mL, mean Cmax of 123 ng/mL, and mean half-life of 27.8 hr. Higher plasma levels in the 6–12 year old group were largely attributable to patients with lower body weights. No gender associated differences were observed. By comparison, a group of 22 separately studied adults between 18 and 45 years of age (11 male, 11 female) received 30 days of 200 mg/day sertraline and exhibited a mean sertraline AUC (0–24 hr) of 2570 ng-hr/mL, mean Cmax of 142 ng/mL, and mean half-life of 27.2 hr. Relative to the adults, both the 6–12 year olds and the 13–17 year olds showed about 22% lower AUC (0–24 hr) and Cmax values when plasma concentration was adjusted for weight. These data suggest that pediatric patients metabolize sertraline with slightly greater efficiency than adults. Nevertheless, lower doses may be advisable for pediatric patients given their lower body weights, especially in very young patients, in order to avoid excessive plasma levels (see DOSAGE AND ADMINISTRATION).

Age

Sertraline plasma clearance in a group of 16 (8 male, 8 female) elderly patients treated for 14 days at a dose of 100 mg/day was approximately 40% lower than in a similarly studied group of younger (25 to 32 y.o.) individuals. Steady-state, therefore, should be achieved after 2 to 3 weeks in older patients. The same study showed a decreased clearance of desmethylsertraline in older males, but not in older females.

Liver Disease

As might be predicted from its primary site of metabolism, liver impairment can affect the elimination of sertraline. In patients with chronic mild liver impairment (N=10, 8 patients with Child-Pugh scores of 5–6 and 2 patients with Child-Pugh scores of 7–8) who received 50 mg sertraline per day maintained for 21 days, sertraline clearance was reduced, resulting in approximately 3-fold greater exposure compared to age-matched volunteers with no hepatic impairment (N=10). The exposure to desmethylsertraline was approximately 2-fold greater compared to age-matched volunteers with no hepatic impairment. There were no significant differences in plasma protein binding observed between the two groups. The effects of sertraline in patients with moderate and severe hepatic impairment have not been studied. The results suggest that the use of sertraline in patients with liver disease must be approached with caution. If sertraline is administered to patients with liver impairment, a lower or less frequent dose should be used (see PRECAUTIONS and DOSAGE AND ADMINISTRATION).

Renal Disease

Sertraline is extensively metabolized and excretion of unchanged drug in urine is a minor route of elimination. In volunteers with mild to moderate (CLcr=30–60 mL/min), moderate to severe (CLcr=10–29 mL/min) or severe (receiving hemodialysis) renal impairment (N=10 each group), the pharmacokinetics and protein binding of 200 mg sertraline per day maintained for 21 days were not altered compared to age-matched volunteers (N=12) with no renal impairment. Thus sertraline multiple dose pharmacokinetics appear to be unaffected by renal impairment (see PRECAUTIONS).

Clinical Trials

Major Depressive Disorder

The efficacy of sertraline hydrochloride as a treatment for major depressive disorder was established in two placebo-controlled studies in adult outpatients meeting DSM-III criteria for major depressive disorder. Study 1 was an 8-week study with flexible dosing of sertraline hydrochloride in a range of 50 to 200 mg/day; the mean dose for completers was 145 mg/day. Study 2 was a 6-week fixed-dose study, including sertraline hydrochloride doses of 50, 100, and 200 mg/day. Overall, these studies demonstrated sertraline hydrochloride to be superior to placebo on the Hamilton Depression Rating Scale and the Clinical Global Impression Severity and Improvement scales. Study 2 was not readily interpretable regarding a dose response relationship for effectiveness.

Study 3 involved depressed outpatients who had responded by the end of an initial 8-week open treatment phase on sertraline hydrochloride 50–200 mg/day. These patients (N=295) were randomized to continuation for 44 weeks on double-blind sertraline hydrochloride 50–200 mg/day or placebo. A statistically significantly lower relapse rate was observed for patients taking sertraline hydrochloride compared to those on placebo. The mean dose for completers was 70 mg/day.

Analyses for gender effects on outcome did not suggest any differential responsiveness on the basis of sex.

Obsessive-Compulsive Disorder (OCD)

The effectiveness of sertraline hydrochloride in the treatment of OCD was demonstrated in three multicenter placebo-controlled studies of adult outpatients (Studies 1–3). Patients in all studies had moderate to severe OCD (DSM-III or DSM-III-R) with mean baseline ratings on the Yale–Brown Obsessive-Compulsive Scale (YBOCS) total score ranging from 23 to 25.

Study 1 was an 8-week study with flexible dosing of sertraline hydrochloride in a range of 50 to 200 mg/day; the mean dose for completers was 186 mg/day. Patients receiving sertraline hydrochloride experienced a mean reduction of approximately 4 points on the YBOCS total score which was significantly greater than the mean reduction of 2 points in placebo-treated patients.

Study 2 was a 12-week fixed-dose study, including sertraline hydrochloride doses of 50, 100, and 200 mg/day. Patients receiving sertraline hydrochloride doses of 50 and 200 mg/day experienced mean reductions of approximately 6 points on the YBOCS total score which were significantly greater than the approximately 3 point reduction in placebo-treated patients.

Study 3 was a 12-week study with flexible dosing of sertraline hydrochloride in a range of 50 to 200 mg/day; the mean dose for completers was 185 mg/day. Patients receiving sertraline hydrochloride experienced a mean reduction of approximately 7 points on the YBOCS total score which was significantly greater than the mean reduction of approximately 4 points in placebo-treated patients.

Analyses for age and gender effects on outcome did not suggest any differential responsiveness on the basis of age or sex.

The effectiveness of sertraline hydrochloride for the treatment of OCD was also demonstrated in a 12-week, multicenter, placebo-controlled, parallel group study in a pediatric outpatient population (children and adolescents, ages 6–17). Patients receiving sertraline hydrochloride in this study were initiated at doses of either 25 mg/day (children, ages 6–12) or 50 mg/day (adolescents, ages 13–17), and then titrated over the next four weeks to a maximum dose of 200 mg/day, as tolerated. The mean dose for completers was 178 mg/day. Dosing was once a day in the morning or evening. Patients in this study had moderate to severe OCD (DSM-III-R) with mean baseline ratings on the Children's Yale-Brown Obsessive-Compulsive Scale (CYBOCS) total score of 22. Patients receiving sertraline experienced a mean reduction of approximately 7 units on the CYBOCS total score which was significantly greater than the 3 unit reduction for placebo patients. Analyses for age and gender effects on outcome did not suggest any differential responsiveness on the basis of age or sex.

In a longer-term study, patients meeting DSM-III-R criteria for OCD who had responded during a 52-week single-blind trial on sertraline hydrochloride 50–200 mg/day (n=224) were randomized to continuation of sertraline hydrochloride or to substitution of placebo for up to 28 weeks of observation for discontinuation due to relapse or insufficient clinical response. Response during the single-blind phase was defined as a decrease in the YBOCS score of ≥ 25% compared to baseline and a CGI-I of 1 (very much improved), 2 (much improved) or 3 (minimally improved). Relapse during the double-blind phase was defined as the following conditions being met (on three consecutive visits for 1 and 2, and for visit 3 for condition 3): (1) YBOCS score increased by ≥ 5 points, to a minimum of 20, relative to baseline; (2) CGI-I increased by ≥ one point; and (3) worsening of the patient's condition in the investigator's judgment, to justify alternative treatment. Insufficient clinical response indicated a worsening of the patient's condition that resulted in study discontinuation, as assessed by the investigator. Patients receiving continued sertraline hydrochloride treatment experienced a significantly lower rate of discontinuation due to relapse or insufficient clinical response over the subsequent 28 weeks compared to those receiving placebo. This pattern was demonstrated in male and female subjects.

Panic Disorder

The effectiveness of sertraline hydrochloride in the treatment of panic disorder was demonstrated in three double-blind, placebo-controlled studies (Studies 1–3) of adult outpatients who had a primary diagnosis of panic disorder (DSM-III-R), with or without agoraphobia.

Studies 1 and 2 were 10-week flexible dose studies. Sertraline hydrochloride was initiated at 25 mg/day for the first week, and then patients were dosed in a range of 50–200 mg/day on the basis of clinical response and toleration. The mean sertraline hydrochloride doses for completers to 10 weeks were 131 mg/day and 144 mg/day, respectively, for Studies 1 and 2. In these studies, sertraline hydrochloride was shown to be significantly more effective than placebo on change from baseline in panic attack frequency and on the Clinical Global Impression Severity of Illness and Global Improvement scores. The difference between sertraline hydrochloride and placebo in reduction from baseline in the number of full panic attacks was approximately 2 panic attacks per week in both studies.

Study 3 was a 12-week fixed-dose study, including sertraline hydrochloride doses of 50, 100, and 200 mg/day. Patients receiving sertraline hydrochloride experienced a significantly greater reduction in panic attack frequency than patients receiving placebo. Study 3 was not readily interpretable regarding a dose response relationship for effectiveness.

Subgroup analyses did not indicate that there were any differences in treatment outcomes as a function of age, race, or gender.

In a longer-term study, patients meeting DSM-III-R criteria for Panic Disorder who had responded during a 52-week open trial on sertraline hydrochloride 50–200 mg/day (n=183) were randomized to continuation of sertraline hydrochloride or to substitution of placebo for up to 28 weeks of observation for discontinuation due to relapse or insufficient clinical response. Response during the open phase was defined as a CGI-I score of 1(very much improved) or 2 (much improved). Relapse during the double-blind phase was defined as the following conditions being met on three consecutive visits: (1) CGI-I ≥ 3; (2) meets DSM-III-R criteria for Panic Disorder; (3) number of panic attacks greater than at baseline. Insufficient clinical response indicated a worsening of the patient's condition that resulted in study discontinuation, as assessed by the investigator. Patients receiving continued sertraline hydrochloride treatment experienced a significantly lower rate of discontinuation due to relapse or insufficient clinical response over the subsequent 28 weeks compared to those receiving placebo. This pattern was demonstrated in male and female subjects.

Posttraumatic Stress Disorder (PTSD)

The effectiveness of sertraline hydrochloride in the treatment of PTSD was established in two multicenter placebo-controlled studies (Studies 1–2) of adult outpatients who met DSM-III-R criteria for PTSD. The mean duration of PTSD for these patients was 12 years (Studies 1 and 2 combined) and 44% of patients (169 of the 385 patients treated) had secondary depressive disorder.

Studies 1 and 2 were 12-week flexible dose studies. Sertraline hydrochloride was initiated at 25 mg/day for the first week, and patients were then dosed in the range of 50–200 mg/day on the basis of clinical response and toleration. The mean sertraline hydrochloride dose for completers was 146 mg/day and 151 mg/day, respectively, for Studies 1 and 2. Study outcome was assessed by the Clinician-Administered PTSD Scale Part 2 (CAPS) which is a multi-item instrument that measures the three PTSD diagnostic symptom clusters of reexperiencing/intrusion, avoidance/numbing, and hyperarousal as well as the patient-rated Impact of Event Scale (IES) which measures intrusion and avoidance symptoms. Sertraline hydrochloride was shown to be significantly more effective than placebo on change from baseline to endpoint on the CAPS, IES and on the Clinical Global Impressions (CGI) Severity of Illness and Global Improvement scores. In two additional placebo-controlled PTSD trials, the difference in response to treatment between patients receiving sertraline hydrochloride and patients receiving placebo was not statistically significant. One of these additional studies was conducted in patients similar to those recruited for Studies 1 and 2, while the second additional study was conducted in predominantly male veterans.

As PTSD is a more common disorder in women than men, the majority (76%) of patients in these trials were women (152 and 139 women on sertraline and placebo versus 39 and 55 men on sertraline and placebo; Studies 1 and 2 combined). Post hoc exploratory analyses revealed a significant difference between sertraline hydrochloride and placebo on the CAPS, IES and CGI in women, regardless of baseline diagnosis of comorbid major depressive disorder, but essentially no effect in the relatively smaller number of men in these studies. The clinical significance of this apparent gender interaction is unknown at this time. There was insufficient information to determine the effect of race or age on outcome.

In a longer-term study, patients meeting DSM-III-R criteria for PTSD who had responded during a 24-week open trial on sertraline hydrochloride 50–200 mg/day (n=96) were randomized to continuation of sertraline hydrochloride or to substitution of placebo for up to 28 weeks of observation for relapse. Response during the open phase was defined as a CGI-I of 1 (very much improved) or 2 (much improved), and a decrease in the CAPS-2 score of > 30% compared to baseline. Relapse during the double-blind phase was defined as the following conditions being met on two consecutive visits: (1) CGI-I ≥ 3; (2) CAPS-2 score increased by ≥ 30% and by ≥ 15 points relative to baseline; and (3) worsening of the patient's condition in the investigator's judgment. Patients receiving continued sertraline hydrochloride treatment experienced significantly lower relapse rates over the subsequent 28 weeks compared to those receiving placebo. This pattern was demonstrated in male and female subjects.

Premenstrual Dysphoric Disorder (PMDD)

The effectiveness of sertraline hydrochloride for the treatment of PMDD was established in two double-blind, parallel group, placebo-controlled flexible dose trials (Studies 1 and 2) conducted over 3 menstrual cycles. Patients in Study 1 met DSM-III-R criteria for Late Luteal Phase Dysphoric Disorder (LLPDD), the clinical entity now referred to as Premenstrual Dysphoric Disorder (PMDD) in DSM-IV. Patients in Study 2 met DSM-IV criteria for PMDD. Study 1 utilized daily dosing throughout the study, while Study 2 utilized luteal phase dosing for the 2 weeks prior to the onset of menses. The mean duration of PMDD symptoms for these patients was approximately 10.5 years in both studies. Patients on oral contraceptives were excluded from these trials; therefore, the efficacy of sertraline in combination with oral contraceptives for the treatment of PMDD is unknown.

Efficacy was assessed with the Daily Record of Severity of Problems (DRSP), a patient-rated instrument that mirrors the diagnostic criteria for PMDD as identified in the DSM-IV, and includes assessments for mood, physical symptoms, and other symptoms. Other efficacy assessments included the Hamilton Depression Rating Scale (HAMD-17), and the Clinical Global Impression Severity of Illness (CGI-S) and Improvement (CGI-I) scores.

In Study 1, involving n=251 randomized patients; sertraline hydrochloride treatment was initiated at 50 mg/day and administered daily throughout the menstrual cycle. In subsequent cycles, patients were dosed in the range of 50–150 mg/day on the basis of clinical response and toleration. The mean dose for completers was 102 mg/day. Sertraline hydrochloride administered daily throughout the menstrual cycle was significantly more effective than placebo on change from baseline to endpoint on the DRSP total score, the HAMD-17 total score, and the CGI-S score, as well as the CGI-I score at endpoint.

In Study 2, involving n=281 randomized patients, sertraline hydrochloride treatment was initiated at 50 mg/day in the late luteal phase (last 2 weeks) of each menstrual cycle and then discontinued at the onset of menses. In subsequent cycles, patients were dosed in the range of 50–100 mg/day in the luteal phase of each cycle, on the basis of clinical response and toleration. Patients who were titrated to 100 mg/day received 50 mg/day for the first 3 days of the cycle, then 100 mg/day for the remainder of the cycle. The mean sertraline hydrochloride dose for completers was 74 mg/day. Sertraline hydrochloride administered in the late luteal phase of the menstrual cycle was significantly more effective than placebo on change from baseline to endpoint on the DRSP total score and the CGI-S score, as well as the CGI-I score at endpoint.

There was insufficient information to determine the effect of race or age on outcome in these studies.

Social Anxiety Disorder

The effectiveness of sertraline hydrochloride in the treatment of social anxiety disorder (also known as social phobia) was established in two multicenter placebo-controlled studies (Study 1 and 2) of adult outpatients who met DSM-IV criteria for social anxiety disorder.

Study 1 was a 12-week, multicenter, flexible dose study comparing sertraline hydrochloride (50–200 mg/day) to placebo, in which sertraline hydrochloride was initiated at 25 mg/day for the first week. Study outcome was assessed by (a) the Liebowitz Social Anxiety Scale (LSAS), a 24-item clinician administered instrument that measures fear, anxiety and avoidance of social and performance situations, and by (b) the proportion of responders as defined by the Clinical Global Impression of Improvement (CGI-I) criterion of CGI-I ≤ 2 (very much or much improved). Sertraline hydrochloride was statistically significantly more effective than placebo as measured by the LSAS and the percentage of responders.

Study 2 was a 20-week, multicenter, flexible dose study that compared sertraline hydrochloride (50–200 mg/day) to placebo. Study outcome was assessed by the (a) Duke Brief Social Phobia Scale (BSPS), a multi-item clinician-rated instrument that measures fear, avoidance and physiologic response to social or performance situations, (b) the Marks Fear Questionnaire Social Phobia Subscale (FQ-SPS), a 5-item patient-rated instrument that measures change in the severity of phobic avoidance and distress, and (c) the CGI-I responder criterion of ≤ 2. Sertraline hydrochloride was shown to be statistically significantly more effective than placebo as measured by the BSPS total score and fear, avoidance and physiologic factor scores, as well as the FQ-SPS total score, and to have significantly more responders than placebo as defined by the CGI-I.

Subgroup analyses did not suggest differences in treatment outcome on the basis of gender. There was insufficient information to determine the effect of race or age on outcome.

In a longer-term study, patients meeting DSM-IV criteria for social anxiety disorder who had responded while assigned to sertraline hydrochloride (CGI-I of 1 or 2) during a 20-week placebo-controlled trial on sertraline hydrochloride 50–200 mg/day were randomized to continuation of sertraline hydrochloride or to substitution of placebo for up to 24 weeks of observation for relapse. Relapse was defined as ≥ 2 point increase in the Clinical Global Impression – Severity of Illness (CGI-S) score compared to baseline or study discontinuation due to lack of efficacy. Patients receiving sertraline hydrochloride continuation treatment experienced a statistically significantly lower relapse rate over this 24-week study than patients randomized to placebo substitution.

INDICATIONS AND USAGE

Major Depressive Disorder

Sertraline hydrochloride is indicated for the treatment of major depressive disorder in adults.

The efficacy of sertraline hydrochloride in the treatment of a major depressive episode was established in six to eight week controlled trials of adult outpatients whose diagnoses corresponded most closely to the DSM-III category of major depressive disorder (see Clinical Trials under CLINICAL PHARMACOLOGY).

A major depressive episode implies a prominent and relatively persistent depressed or dysphoric mood that usually interferes with daily functioning (nearly every day for at least 2 weeks); it should include at least 4 of the following 8 symptoms: change in appetite, change in sleep, psychomotor agitation or retardation, loss of interest in usual activities or decrease in sexual drive, increased fatigue, feelings of guilt or worthlessness, slowed thinking or impaired concentration, and a suicide attempt or suicidal ideation.

The antidepressant action of sertraline hydrochloride in hospitalized depressed patients has not been adequately studied.

The efficacy of sertraline hydrochloride in maintaining an antidepressant response for up to 44 weeks following 8 weeks of open-label acute treatment (52 weeks total) was demonstrated in a placebo-controlled trial. The usefulness of the drug in patients receiving sertraline hydrochloride for extended periods should be reevaluated periodically (see Clinical Trials under CLINICAL PHARMACOLOGY).

Obsessive-Compulsive Disorder

Sertraline hydrochloride is indicated for the treatment of obsessions and compulsions in patients with obsessive-compulsive disorder (OCD), as defined in the DSM-III-R; i.e., the obsessions or compulsions cause marked distress, are time-consuming, or significantly interfere with social or occupational functioning.

The efficacy of sertraline hydrochloride was established in 12-week trials with obsessive-compulsive outpatients having diagnoses of obsessive-compulsive disorder as defined according to DSM-III or DSM-III-R criteria (see Clinical Trials under CLINICAL PHARMACOLOGY).

Obsessive-compulsive disorder is characterized by recurrent and persistent ideas, thoughts, impulses, or images (obsessions) that are ego-dystonic and/or repetitive, purposeful, and intentional behaviors (compulsions) that are recognized by the person as excessive or unreasonable.

The efficacy of sertraline hydrochloride in maintaining a response, in patients with OCD who responded during a 52-week treatment phase while taking sertraline hydrochloride and were then observed for relapse during a period of up to 28 weeks, was demonstrated in a placebo-controlled trial (see Clinical Trials under CLINICAL PHARMACOLOGY). Nevertheless, the physician who elects to use sertraline hydrochloride for extended periods should periodically re-evaluate the long-term usefulness of the drug for the individual patient (see DOSAGE AND ADMINISTRATION).

Panic Disorder

Sertraline hydrochloride is indicated for the treatment of panic disorder in adults, with or without agoraphobia, as defined in DSM-IV. Panic disorder is characterized by the occurrence of unexpected panic attacks and associated concern about having additional attacks, worry about the implications or consequences of the attacks, and/or a significant change in behavior related to the attacks.

The efficacy of sertraline hydrochloride was established in three 10–12 week trials in adult panic disorder patients whose diagnoses corresponded to the DSM-III-R category of panic disorder (see Clinical Trials under CLINICAL PHARMACOLOGY).

Panic disorder (DSM-IV) is characterized by recurrent unexpected panic attacks, i.e., a discrete period of intense fear or discomfort in which four (or more) of the following symptoms develop abruptly and reach a peak within 10 minutes: (1) palpitations, pounding heart, or accelerated heart rate; (2) sweating; (3) trembling or shaking; (4) sensations of shortness of breath or smothering; (5) feeling of choking; (6) chest pain or discomfort; (7) nausea or abdominal distress; (8) feeling dizzy, unsteady, lightheaded, or faint; (9) derealization (feelings of unreality) or depersonalization (being detached from oneself); (10) fear of losing control; (11) fear of dying; (12) paresthesias (numbness or tingling sensations); (13) chills or hot flushes.

The efficacy of sertraline hydrochloride in maintaining a response, in adult patients with panic disorder who responded during a 52-week treatment phase while taking sertraline hydrochloride and were then observed for relapse during a period of up to 28 weeks, was demonstrated in a placebo-controlled trial (see Clinical Trials under CLINICAL PHARMACOLOGY). Nevertheless, the physician who elects to use sertraline hydrochloride for extended periods should periodically re-evaluate the long-term usefulness of the drug for the individual patient (see DOSAGE AND ADMINISTRATION).

Posttraumatic Stress Disorder (PTSD)

Sertraline hydrochloride is indicated for the treatment of posttraumatic stress disorder in adults.

The efficacy of sertraline hydrochloride in the treatment of PTSD was established in two 12-week placebo-controlled trials of adult outpatients whose diagnosis met criteria for the DSM-III-R category of PTSD (see Clinical Trials under CLINICAL PHARMACOLOGY).

PTSD, as defined by DSM-III-R/IV, requires exposure to a traumatic event that involved actual or threatened death or serious injury, or threat to the physical integrity of self or others, and a response which involves intense fear, helplessness, or horror. Symptoms that occur as a result of exposure to the traumatic event include reexperiencing of the event in the form of intrusive thoughts, flashbacks or dreams, and intense psychological distress and physiological reactivity on exposure to cues to the event; avoidance of situations reminiscent of the traumatic event, inability to recall details of the event, and/or numbing of general responsiveness manifested as diminished interest in significant activities, estrangement from others, restricted range of affect, or sense of foreshortened future; and symptoms of autonomic arousal including hypervigilance, exaggerated startle response, sleep disturbance, impaired concentration, and irritability or outbursts of anger. A PTSD diagnosis requires that the symptoms are present for at least a month and that they cause clinically significant distress or impairment in social, occupational, or other important areas of functioning.

The efficacy of sertraline hydrochloride in maintaining a response in adult patients with PTSD for up to 28 weeks following 24 weeks of open-label treatment was demonstrated in a placebo-controlled trial. Nevertheless, the physician who elects to use sertraline hydrochloride for extended periods should periodically re-evaluate the long-term usefulness of the drug for the individual patient (see DOSAGE AND ADMINISTRATION).

Premenstrual Dysphoric Disorder (PMDD)

Sertraline hydrochloride is indicated for the treatment of premenstrual dysphoric disorder (PMDD) in adults.

The efficacy of sertraline hydrochloride in the treatment of PMDD was established in 2 placebo-controlled trials of female adult outpatients treated for 3 menstrual cycles who met criteria for the DSM-III-R/IV category of PMDD (see Clinical Trials under CLINICAL PHARMACOLOGY).

The essential features of PMDD include markedly depressed mood, anxiety or tension, affective lability, and persistent anger or irritability. Other features include decreased interest in activities, difficulty concentrating, lack of energy, change in appetite or sleep, and feeling out of control. Physical symptoms associated with PMDD include breast tenderness, headache, joint and muscle pain, bloating and weight gain. These symptoms occur regularly during the luteal phase and remit within a few days following onset of menses; the disturbance markedly interferes with work or school or with usual social activities and relationships with others. In making the diagnosis, care should be taken to rule out other cyclical mood disorders that may be exacerbated by treatment with an antidepressant.

The effectiveness of sertraline hydrochloride in long-term use, that is, for more than 3 menstrual cycles, has not been systematically evaluated in controlled trials. Therefore, the physician who elects to use sertraline hydrochloride for extended periods should periodically re-evaluate the long-term usefulness of the drug for the individual patient (see DOSAGE AND ADMINISTRATION).

Social Anxiety Disorder

Sertraline hydrochloride is indicated for the treatment of social anxiety disorder, also known as social phobia in adults.

The efficacy of sertraline hydrochloride in the treatment of social anxiety disorder was established in two placebo-controlled trials of adult outpatients with a diagnosis of social anxiety disorder as defined by DSM-IV criteria (see Clinical Trials under CLINICAL PHARMACOLOGY).

Social anxiety disorder, as defined by DSM-IV, is characterized by marked and persistent fear of social or performance situations involving exposure to unfamiliar people or possible scrutiny by others and by fears of acting in a humiliating or embarrassing way. Exposure to the feared social situation almost always provokes anxiety and feared social or performance situations are avoided or else are endured with intense anxiety or distress. In addition, patients recognize that the fear is excessive or unreasonable and the avoidance and anticipatory anxiety of the feared situation is associated with functional impairment or marked distress.

The efficacy of sertraline hydrochloride in maintaining a response in adult patients with social anxiety disorder for up to 24 weeks following 20 weeks of sertraline hydrochloride treatment was demonstrated in a placebo-controlled trial. Physicians who prescribe sertraline hydrochloride for extended periods should periodically re-evaluate the long-term usefulness of the drug for the individual patient (see Clinical Trials under CLINICAL PHARMACOLOGY).

CONTRAINDICATIONS

All Dosage Forms of sertraline hydrochloride

Concomitant use in patients taking monoamine oxidase inhibitors (MAOIs) is contraindicated (see WARNINGS). Concomitant use in patients taking pimozide is contraindicated (see PRECAUTIONS).

Sertraline hydrochloride is contraindicated in patients with a hypersensitivity to sertraline or any of the inactive ingredients in sertraline hydrochloride.

Oral Concentrate

Sertraline hydrochloride oral concentrate is contraindicated with ANTABUSE (disulfiram) due to the alcohol content of the concentrate.

WARNINGS

Clinical Worsening and Suicide Risk

Patients with major depressive disorder (MDD), both adult and pediatric, may experience worsening of their depression and/or the emergence of suicidal ideation and behavior (suicidality) or unusual changes in behavior, whether or not they are taking antidepressant medications, and this risk may persist until significant remission occurs. Suicide is a known risk of depression and certain other psychiatric disorders, and these disorders themselves are the strongest predictors of suicide. There has been a long-standing concern, however, that antidepressants may have a role in inducing worsening of depression and the emergence of suicidality in certain patients during the early phases of treatment. Pooled analyses of short-term placebo-controlled trials of antidepressant drugs (SSRIs and others) showed that these drugs increase the risk of suicidal thinking and behavior (suicidality) in children, adolescents, and young adults (ages 18–24) with major depressive disorder (MDD) and other psychiatric disorders. Short-term studies did not show an increase in the risk of suicidality with antidepressants compared to placebo in adults beyond age 24; there was a reduction with antidepressants compared to placebo in adults aged 65 and older.

The pooled analyses of placebo-controlled trials in children and adolescents with MDD, obsessive compulsive disorder (OCD), or other psychiatric disorders included a total of 24 short-term trials of 9 antidepressant drugs in over 4400 patients. The pooled analyses of placebo-controlled trials in adults with MDD or other psychiatric disorders included a total of 295 short-term trials (median duration of 2 months) of 11 antidepressant drugs in over 77,000 patients. There was considerable variation in risk of suicidality among drugs, but a tendency toward an increase in the younger patients for almost all drugs studied. There were differences in absolute risk of suicidality across the different indications, with the highest incidence in MDD. The risk differences (drug vs. placebo), however, were relatively stable within age strata and across indications. These risk differences (drug-placebo difference in the number of cases of suicidality per 1000 patients treated) are provided in Table 1.

Table 1
Age Range | Drug-Placebo Difference in Number of Cases of Suicidality per 1000 Patients Treated
 | Increases Compared to Placebo
<18 | 14 additional cases
18–24 | 5 additional cases
 | Decreases Compared to Placebo
25–64 | 1 fewer case
≥65 | 6 fewer cases

No suicides occurred in any of the pediatric trials. There were suicides in the adult trials, but the number was not sufficient to reach any conclusion about drug effect on suicide.

It is unknown whether the suicidality risk extends to longer-term use, i.e., beyond several months. However, there is substantial evidence from placebo-controlled maintenance trials in adults with depression that the use of antidepressants can delay the recurrence of depression.

All patients being treated with antidepressants for any indication should be monitored appropriately and observed closely for clinical worsening, suicidality, and unusual changes in behavior, especially during the initial few months of a course of drug therapy, or at times of dose changes, either increases or decreases.

The following symptoms, anxiety, agitation, panic attacks, insomnia, irritability, hostility aggressiveness, impulsivity, akathisia (psychomotor restlessness), hypomania, and mania, have been reported in adult and pediatric patients being treated with antidepressants for major depressive disorder as well as for other indications, both psychiatric and nonpsychiatric. Although a causal link between the emergence of such symptoms and either the worsening of depression and/or the emergence of suicidal impulses has not been established, there is concern that such symptoms may represent precursors to emerging suicidality.

Consideration should be given to changing the therapeutic regimen, including possibly discontinuing the medication, in patients whose depression is persistently worse, or who are experiencing emergent suicidality or symptoms that might be precursors to worsening depression or suicidality, especially if these symptoms are severe, abrupt in onset, or were not part of the patient's presenting symptoms.

If the decision has been made to discontinue treatment, medication should be tapered, as rapidly as is feasible, but with recognition that abrupt discontinuation can be associated with certain symptoms (see PRECAUTIONS and DOSAGE AND ADMINISTRATION—Discontinuation of Treatment with sertraline hydrochloride, for a description of the risks of discontinuation of sertraline hydrochloride).

Families and caregivers of patients being treated with antidepressants for major depressive disorder or other indications, both psychiatric and nonpsychiatric, should be alerted about the need to monitor patients for the emergence of agitation, irritability, unusual changes in behavior, and the other symptoms described above, as well as the emergence of suicidality, and to report such symptoms immediately to health care providers. Such monitoring should include daily observation by families and caregivers. Prescriptions for sertraline hydrochloride should be written for the smallest quantity of tablets consistent with good patient management, in order to reduce the risk of overdose.

Screening Patients for Bipolar Disorder

A major depressive episode may be the initial presentation of bipolar disorder. It is generally believed (though not established in controlled trials) that treating such an episode with an antidepressant alone may increase the likelihood of precipitation of a mixed/manic episode in patients at risk for bipolar disorder. Whether any of the symptoms described above represent such a conversion is unknown. However, prior to initiating treatment with an antidepressant, patients with depressive symptoms should be adequately screened to determine if they are at risk for bipolar disorder; such screening should include a detailed psychiatric history, including a family history of suicide, bipolar disorder, and depression. It should be noted that sertraline hydrochloride is not approved for use in treating bipolar depression.

Cases of serious sometimes fatal reactions have been reported in patients receiving sertraline hydrochloride, a selective serotonin reuptake inhibitor (SSRI), in combination with a monoamine oxidase inhibitor (MAOI). Symptoms of a drug interaction between an SSRI and an MAOI include: hyperthermia, rigidity, myoclonus, autonomic instability with possible rapid fluctuations of vital signs, mental status changes that include confusion, irritability, and extreme agitation progressing to delirium and coma. These reactions have also been reported in patients who have recently discontinued an SSRI and have been started on an MAOI. Some cases presented with features resembling neuroleptic malignant syndrome. Therefore, sertraline hydrochloride should not be used in combination with an MAOI, or within 14 days of discontinuing treatment with an MAOI. Similarly, at least 14 days should be allowed after stopping sertraline hydrochloride before starting an MAOI.

The concomitant use of sertraline hydrochloride with MAOIs intended to treat depression is contraindicated (see CONTRAINDICATIONS and WARNINGS – Potential for Interaction with Monoamine Oxidase Inhibitors).

Serotonin Syndrome or Neuroleptic Malignant Syndrome (NMS)-like Reactions

The development of a potentially life-threatening serotonin syndrome or Neuroleptic Malignant Syndrome (NMS)-like reactions have been reported with SNRIs and SSRIs alone, including Sertraline hydrochloride treatment, but particularly with concomitant use of serotonergic drugs (including triptans) with drugs which impair metabolism of serotonin (including MAOIs), or with antipsychotics or other dopamine antagonists. Serotonin syndrome symptoms may include mental status changes (e.g., agitation, hallucinations, coma), autonomic instability (e.g., tachycardia, labile blood pressure, hyperthermia), neuromuscular aberrations (e.g., hyperreflexia, incoordination) and/or gastrointestinal symptoms (e.g., nausea, vomiting, diarrhea). Serotonin syndrome, in its most severe form can resemble neuroleptic malignant syndrome, which includes hyperthermia, muscle rigidity, autonomic instability with possible rapid fluctuation of vital signs, and mental status changes. Patients should be monitored for the emergence of serotonin syndrome or NMS-like signs and symptoms.

The concomitant use of Sertraline hydrochloride with MAOIs intended to treat depression is contraindicated.

If concomitant treatment of Sertraline hydrochloride with a 5-hydroxytryptamine receptor agonist (triptan) is clinically warranted, careful observation of the patient is advised, particularly during treatment initiation and dose increases.

The concomitant use of Sertraline hydrochloride with serotonin precursors (such as tryptophan) is not recommended.

Treatment with Sertraline hydrochloride and any concomitant serotonergic or antidopaminergic agents, including antipsychotics, should be discontinued immediately if the above events occur and supportive symptomatic treatment should be initiated.

PRECAUTIONS

General

Activation of Mania/Hypomania

During premarketing testing, hypomania or mania occurred in approximately 0.4% of sertraline hydrochloride treated patients.

Weight Loss

Significant weight loss may be an undesirable result of treatment with sertraline for some patients, but on average, patients in controlled trials had minimal, 1 to 2 pound weight loss, versus smaller changes on placebo. Only rarely have sertraline patients been discontinued for weight loss.

Seizure

Sertraline hydrochloride has not been evaluated in patients with a seizure disorder. These patients were excluded from clinical studies during the product's premarket testing. No seizures were observed among approximately 3000 patients treated with sertraline hydrochloride in the development program for major depressive disorder. However, 4 patients out of approximately 1800 (220 <18 years of age) exposed during the development program for obsessive-compulsive disorder experienced seizures, representing a crude incidence of 0.2%. Three of these patients were adolescents, two with a seizure disorder and one with a family history of seizure disorder, none of whom were receiving anticonvulsant medication. Accordingly, sertraline hydrochloride should be introduced with care in patients with a seizure disorder.

Discontinuation of Treatment with sertraline hydrochloride

During marketing of sertraline hydrochloride and other SSRIs and SNRIs (Serotonin and Norepinephrine Reuptake Inhibitors), there have been spontaneous reports of adverse events occurring upon discontinuation of these drugs, particularly when abrupt, including the following: dysphoric mood, irritability, agitation, dizziness, sensory disturbances (e.g. paresthesias such as electric shock sensations), anxiety, confusion, headache, lethargy, emotional lability, insomnia, and hypomania. While these events are generally self-limiting, there have been reports of serious discontinuation symptoms.

Patients should be monitored for these symptoms when discontinuing treatment with sertraline hydrochloride. A gradual reduction in the dose rather than abrupt cessation is recommended whenever possible. If intolerable symptoms occur following a decrease in the dose or upon discontinuation of treatment, then resuming the previously prescribed dose may be considered. Subsequently, the physician may continue decreasing the dose but at a more gradual rate (see DOSAGE AND ADMINISTRATION).

Abnormal Bleeding

SSRIs and SNRIs, including sertraline hydrochloride, may increase the risk of bleeding events. Concomitant use of aspirin, nonsteroidal anti-inflammatory drugs, warfarin, and other anticoagulants may add to this risk. Case reports and epidemiological studies (case-control and cohort design) have demonstrated an association between use of drugs that interfere with serotonin reuptake and the occurrence of gastrointestinal bleeding. Bleeding events related to SSRIs and SNRIs use have ranged from ecchymoses, hematomas, epistaxis, and petechiae to life-threatening hemorrhages.

Patients should be cautioned about the risk of bleeding associated with the concomitant use of Sertraline hydrochloride and NSAIDs, aspirin, or other drugs that affect coagulation.

Weak Uricosuric Effect

Sertraline hydrochloride is associated with a mean decrease in serum uric acid of approximately 7%. The clinical significance of this weak uricosuric effect is unknown.

Use in Patients with Concomitant Illness

Clinical experience with sertraline hydrochloride in patients with certain concomitant systemic illness is limited. Caution is advisable in using sertraline hydrochloride in patients with diseases or conditions that could affect metabolism or hemodynamic responses.

Patients with a recent history of myocardial infarction or unstable heart disease were excluded from clinical studies during the product's premarket testing. However, the electrocardiograms of 774 patients who received sertraline hydrochloride in double-blind trials were evaluated and the data indicate that sertraline hydrochloride is not associated with the development of significant ECG abnormalities.

Sertraline hydrochloride administered in a flexible dose range of 50 to 200 mg/day (mean dose of 89 mg/day) was evaluated in a post-marketing, placebo-controlled trial of 372 randomized subjects with a DSM-IV diagnosis of major depressive disorder and recent history of myocardial infarction or unstable angina requiring hospitalization. Exclusions from this trial included, among others, patients with uncontrolled hypertension, need for cardiac surgery, history of CABG within 3 months of index event, severe or symptomatic bradycardia, non-atherosclerotic cause of angina, clinically significant renal impairment (creatinine > 2.5 mg/dl), and clinically significant hepatic dysfunction. Sertraline hydrochloride treatment initiated during the acute phase of recovery (within 30 days post-MI or post-hospitalization for unstable angina) was indistinguishable from placebo in this study on the following week 16 treatment endpoints: left ventricular ejection fraction, total cardiovascular events (angina, chest pain, edema, palpitations, syncope, postural dizziness, CHF, MI, tachycardia, bradycardia, and changes in BP), and major cardiovascular events involving death or requiring hospitalization (for MI, CHF, stroke, or angina).

Sertraline hydrochloride is extensively metabolized by the liver. In patients with chronic mild liver impairment, sertraline clearance was reduced, resulting in increased AUC, Cmax and elimination half-life. The effects of sertraline in patients with moderate and severe hepatic impairment have not been studied. The use of sertraline in patients with liver disease must be approached with caution. If sertraline is administered to patients with liver impairment, a lower or less frequent dose should be used (see CLINICAL PHARMACOLOGY and DOSAGE AND ADMINISTRATION).

Since sertraline hydrochloride is extensively metabolized, excretion of unchanged drug in urine is a minor route of elimination. A clinical study comparing sertraline pharmacokinetics in healthy volunteers to that in patients with renal impairment ranging from mild to severe (requiring dialysis) indicated that the pharmacokinetics and protein binding are unaffected by renal disease. Based on the pharmacokinetic results, there is no need for dosage adjustment in patients with renal impairment (see CLINICAL PHARMACOLOGY).

Interference with Cognitive and Motor Performance

In controlled studies, sertraline hydrochloride did not cause sedation and did not interfere with psychomotor performance. (See Information for Patients.)

Hyponatremia

Hyponatremia may occur as a result of treatment with SSRIs and SNRIs, including sertraline hydrochloride. In many cases, this hyponatremia appears to be the result of the syndrome of inappropriate antidiuretic hormone secretion (SIADH). Cases with serum sodium lower than 110 mmol/L have been reported. Elderly patients may be at greater risk of developing hyponatremia with SSRIs and SNRIs. Also, patients taking diuretics or who are otherwise volume depleted may be at greater risk (see GERIATRIC USE). Discontinuation of sertraline hydrochloride should be considered in patients with symptomatic hyponatremia and appropriate medical intervention should be instituted.

Signs and symptoms of hyponatremia include headache, difficulty concentrating, memory impairment, confusion, weakness, and unsteadiness, which may lead to falls. Signs and symptoms associated with more severe and/or acute cases have included hallucination, syncope, seizure, coma, respiratory arrest, and death.

Platelet Function

There have been rare reports of altered platelet function and/or abnormal results from laboratory studies in patients taking sertraline hydrochloride. While there have been reports of abnormal bleeding or purpura in several patients taking sertraline hydrochloride, it is unclear whether sertraline hydrochloride had a causative role.

Information for Patients

Prescribers or other health professionals should inform patients, their families, and their caregivers about the benefits and risks associated with treatment with sertraline hydrochloride and should counsel them in its appropriate use. A patient Medication Guide about “Antidepressant Medicines, Depression and other Serious Mental Illness, and Suicidal Thoughts or Actions: is available for sertraline hydrochloride. The prescriber or health professional should instruct patients, their families, and their caregivers to read the Medication Guide and should assist them in understanding its contents. Patients should be given the opportunity to discuss the contents of the Medication Guide and to obtain answers to any questions they may have. The complete text of the Medication Guide is reprinted at the end of this document.

Patients should be advised of the following issues and asked to alert their prescriber if these occur while taking sertraline hydrochloride.

Clinical Worsening and Suicide Risk

Patients, their families, and their caregivers should be encouraged to be alert to the emergence of anxiety, agitation, panic attacks, insomnia, irritability, hostility, aggressiveness, impulsivity, akathisia (psychomotor restlessness), hypomania, mania, other unusual changes in behavior, worsening of depression, and suicidal ideation, especially early during antidepressant treatment and when the dose is adjusted up or down. Families and caregivers of patients should be advised to look for the emergence of such symptoms on a day-to-day basis, since changes may be abrupt. Such symptoms should be reported to the patient's prescriber or health professional, especially if they are severe, abrupt in onset, or were not part of the patient's presenting symptoms. Symptoms such as these may be associated with an increased risk for suicidal thinking and behavior and indicate a need for very close monitoring and possibly changes in the medication.

Patients should be cautioned about the risk of serotonin syndrome with the concomitant use of SNRIs and SSRIs, including sertraline hydrochloride, and triptans, tramadol, or other serotonergic agents.

Patients should be told that although sertraline hydrochloride has not been shown to impair the ability of normal subjects to perform tasks requiring complex motor and mental skills in laboratory experiments, drugs that act upon the central nervous system may affect some individuals adversely. Therefore, patients should be told that until they learn how they respond to sertraline hydrochloride they should be careful doing activities when they need to be alert, such as driving a car or operating machinery.

Patients should be cautioned about the concomitant use of sertraline hydrochloride and NSAIDs, aspirin, warfarin, or other drugs that affect coagulation since combined use of psychotropic drugs that interfere with serotonin reuptake and these agents has been associated with an increased risk of bleeding.

Patients should be told that although sertraline hydrochloride has not been shown in experiments with normal subjects to increase the mental and motor skill impairments caused by alcohol, the concomitant use of sertraline hydrochloride and alcohol is not advised.

Patients should be told that while no adverse interaction of sertraline hydrochloride with over-the-counter (OTC) drug products is known to occur, the potential for interaction exists. Thus, the use of any OTC product should be initiated cautiously according to the directions of use given for the OTC product.

Patients should be advised to notify their physician if they become pregnant or intend to become pregnant during therapy.

Patients should be advised to notify their physician if they are breast feeding an infant.

Sertraline hydrochloride oral concentrate is contraindicated with ANTABUSE (disulfiram) due to the alcohol content of the concentrate.

Sertraline hydrochloride Oral Concentrate contains 20 mg/mL of sertraline (as the hydrochloride) as the active ingredient and 12% alcohol. Sertraline hydrochloride Oral Concentrate must be diluted before use. Just before taking, use the dropper provided to remove the required amount of sertraline hydrochloride Oral Concentrate and mix with 4 oz (1/2 cup) of water, ginger ale, lemon/lime soda, lemonade or orange juice ONLY. Do not mix sertraline hydrochloride Oral Concentrate with anything other than the liquids listed. The dose should be taken immediately after mixing. Do not mix in advance. At times, a slight haze may appear after mixing; this is normal. Note that caution should be exercised for persons with latex sensitivity, as the dropper dispenser contains dry natural rubber.

Laboratory Tests

None.

Drug Interactions

Potential Effects of Coadministration of Drugs Highly Bound to Plasma Proteins

Because sertraline is tightly bound to plasma protein, the administration of sertraline hydrochloride to a patient taking another drug which is tightly bound to protein (e.g., warfarin, digitoxin) may cause a shift in plasma concentrations potentially resulting in an adverse effect. Conversely, adverse effects may result from displacement of protein bound sertraline hydrochloride by other tightly bound drugs.

In a study comparing prothrombin time AUC (0–120 hr) following dosing with warfarin (0.75 mg/kg) before and after 21 days of dosing with either sertraline hydrochloride (50–200 mg/day) or placebo, there was a mean increase in prothrombin time of 8% relative to baseline for sertraline hydrochloride compared to a 1% decrease for placebo (p<0.02). The normalization of prothrombin time for the sertraline hydrochloride group was delayed compared to the placebo group. The clinical significance of this change is unknown. Accordingly, prothrombin time should be carefully monitored when sertraline hydrochloride therapy is initiated or stopped.

Cimetidine

In a study assessing disposition of sertraline hydrochloride (100 mg) on the second of 8 days of cimetidine administration (800 mg daily), there were significant increases in sertraline hydrochloride mean AUC (50%), Cmax (24%) and half-life (26%) compared to the placebo group. The clinical significance of these changes is unknown.

CNS Active Drugs

In a study comparing the disposition of intravenously administered diazepam before and after 21 days of dosing with either sertraline hydrochloride (50 to 200 mg/day escalating dose) or placebo, there was a 32% decrease relative to baseline in diazepam clearance for the sertraline hydrochloride group compared to a 19% decrease relative to baseline for the placebo group (p<0.03). There was a 23% increase in Tmax for desmethyldiazepam in the sertraline hydrochloride group compared to a 20% decrease in the placebo group (p<0.03). The clinical significance of these changes is unknown.

In a placebo-controlled trial in normal volunteers, the administration of two doses of sertraline hydrochloride did not significantly alter steady-state lithium levels or the renal clearance of lithium.

Nonetheless, at this time, it is recommended that plasma lithium levels be monitored following initiation of sertraline hydrochloride therapy with appropriate adjustments to the lithium dose.

In a controlled study of a single dose (2 mg) of pimozide, 200 mg sertraline (q.d.) co-administration to steady state was associated with a mean increase in pimozide AUC and Cmax of about 40%, but was not associated with any changes in EKG. Since the highest recommended pimozide dose (10 mg) has not been evaluated in combination with sertraline, the effect on QT interval and PK parameters at doses higher than 2 mg at this time are not known. While the mechanism of this interaction is unknown, due to the narrow therapeutic index of pimozide and due to the interaction noted at a low dose of pimozide, concomitant administration of sertraline hydrochloride and pimozide should be contraindicated (see CONTRAINDICATIONS).

Results of a placebo-controlled trial in normal volunteers suggest that chronic administration of sertraline 200 mg/day does not produce clinically important inhibition of phenytoin metabolism. Nonetheless, at this time, it is recommended that plasma phenytoin concentrations be monitored following initiation of sertraline hydrochloride therapy with appropriate adjustments to the phenytoin dose, particularly in patients with multiple underlying medical conditions and/or those receiving multiple concomitant medications.

The effect of sertraline hydrochloride on valproate levels has not been evaluated in clinical trials. In the absence of such data, it is recommended that plasma valproate levels be monitored following initiation of sertraline hydrochloride therapy with appropriate adjustments to the valproate dose.

The risk of using sertraline hydrochloride in combination with other CNS active drugs has not been systematically evaluated. Consequently, caution is advised if the concomitant administration of sertraline hydrochloride and such drugs is required.

There is limited controlled experience regarding the optimal timing of switching from other drugs effective in the treatment of major depressive disorder, obsessive-compulsive disorder, panic disorder, posttraumatic stress disorder, premenstrual dysphoric disorder and social anxiety disorder to sertraline hydrochloride. Care and prudent medical judgment should be exercised when switching, particularly from long-acting agents. The duration of an appropriate washout period which should intervene before switching from one selective serotonin reuptake inhibitor (SSRI) to another has not been established.

Monoamine Oxidase Inhibitors

See CONTRAINDICATIONS and WARNINGS.

Drugs Metabolized by P450 3A4

In three separate in vivo interaction studies, sertraline was co-administered with cytochrome P450 3A4 substrates, terfenadine, carbamazepine, or cisapride under steady-state conditions. The results of these studies indicated that sertraline did not increase plasma concentrations of terfenadine, carbamazepine, or cisapride. These data indicate that sertraline's extent of inhibition of P450 3A4 activity is not likely to be of clinical significance. Results of the interaction study with cisapride indicate that sertraline 200 mg (q.d.) induces the metabolism of cisapride (cisapride AUC and Cmax were reduced by about 35%).

Drugs Metabolized by P450 2D6

Many drugs effective in the treatment of major depressive disorder, e.g., the SSRIs, including sertraline, and most tricyclic antidepressant drugs effective in the treatment of major depressive disorder inhibit the biochemical activity of the drug metabolizing isozyme cytochrome P450 2D6 (debrisoquin hydroxylase), and, thus, may increase the plasma concentrations of co-administered drugs that are metabolized by P450 2D6. The drugs for which this potential interaction is of greatest concern are those metabolized primarily by 2D6 and which have a narrow therapeutic index, e.g., the tricyclic antidepressant drugs effective in the treatment of major depressive disorder and the Type 1C antiarrhythmics propafenone and flecainide. The extent to which this interaction is an important clinical problem depends on the extent of the inhibition of P450 2D6 by the antidepressant and the therapeutic index of the co-administered drug. There is variability among the drugs effective in the treatment of major depressive disorder in the extent of clinically important 2D6 inhibition, and in fact sertraline at lower doses has a less prominent inhibitory effect on 2D6 than some others in the class. Nevertheless, even sertraline has the potential for clinically important 2D6 inhibition. Consequently, concomitant use of a drug metabolized by P450 2D6 with sertraline hydrochloride may require lower doses than usually prescribed for the other drug. Furthermore, whenever sertraline hydrochloride is withdrawn from co-therapy, an increased dose of the co-administered drug may be required (see Tricyclic Antidepressant Drugs Effective in the Treatment of Major Depressive Disorder under PRECAUTIONS).

Serotonergic Drugs

Based on the mechanism of action of SNRIs and SSRIs, including sertraline hydrochloride, and the potential for serotonin syndrome, caution is advised when SNRIs and SSRIs, including sertraline hydrochloride, are coadministered with other drugs that may affect the serotonergic neutrotransmitter systems, such as triptans, linezolid (an antibiotic which is a reversible non-selective MAOI), lithium, tramadol, or St. John's Wort (see WARNINGS-Serotonin Syndrome). The concomitant use of sertraline hydrochloride with other SSRIs, SNRIs or tryptophan is not recommended (see PRECAUTIONS – Drug Interactions).

Triptans

There have been rare post marketing reports of serotonin syndrome with use of an SNRI or an SSRI and a triptan. If concomitant treatment of SNRIs and SSRIs, including sertraline hydrochloride, with a triptan is clinically warranted, careful observation of the patient is advised, particularly during treatment initiation and dose increases (see WARNINGS – Serotonin Syndrome).

Sumatriptan

There have been rare post marketing reports describing patients with weakness, hyperreflexia, and incoordination following the use of a selective serotonin reuptake inhibitor (SSRI) and sumatriptan. If concomitant treatment with sumatriptan and an SSRI (e.g., citalopram, fluoxetine, fluvoxamine, paroxetine, sertraline) is clinically warranted, appropriate observation of the patient is advised.

Tricyclic Antidepressant Drugs Effective in the Treatment of Major Depressive Disorder (TCAs)

The extent to which SSRI–TCA interactions may pose clinical problems will depend on the degree of inhibition and the pharmacokinetics of the SSRI involved. Nevertheless, caution is indicated in the co-administration of TCAs with sertraline hydrochloride, because sertraline may inhibit TCA metabolism. Plasma TCA concentrations may need to be monitored, and the dose of TCA may need to be reduced, if a TCA is co-administered with sertraline hydrochloride (see Drugs Metabolized by P450 2D6 under PRECAUTIONS).

Hypoglycemic Drugs

In a placebo-controlled trial in normal volunteers, administration of sertraline hydrochloride for 22 days (including 200 mg/day for the final 13 days) caused a statistically significant 16% decrease from baseline in the clearance of tolbutamide following an intravenous 1000 mg dose. Sertraline hydrochloride administration did not noticeably change either the plasma protein binding or the apparent volume of distribution of tolbutamide, suggesting that the decreased clearance was due to a change in the metabolism of the drug. The clinical significance of this decrease in tolbutamide clearance is unknown.

Atenolol

Sertraline hydrochloride (100 mg) when administered to 10 healthy male subjects had no effect on the beta-adrenergic blocking ability of atenolol.

Digoxin

In a placebo-controlled trial in normal volunteers, administration of sertraline hydrochloride for 17 days (including 200 mg/day for the last 10 days) did not change serum digoxin levels or digoxin renal clearance.

Microsomal Enzyme Induction

Preclinical studies have shown sertraline hydrochloride to induce hepatic microsomal enzymes. In clinical studies, sertraline hydrochloride was shown to induce hepatic enzymes minimally as determined by a small (5%) but statistically significant decrease in antipyrine half-life following administration of 200 mg/day for 21 days. This small change in antipyrine half-life reflects a clinically insignificant change in hepatic metabolism.

Drugs That Interfere With Hemostasis (Non-selective NSAIDs, Aspirin, Warfarin, etc.)

Serotonin release by platelets plays an important role in hemostasis. Epidemiological studies of the case-control and cohort design that have demonstrated an association between use of psychotropic drugs that interfere with serotonin reuptake and the occurrence of upper gastrointestinal bleeding have also shown that concurrent use of an NSAID or aspirin may potentiate this risk of bleeding. These studies have also shown that concurrent use of an NSAID or aspirin may potentiate this risk of bleeding. Altered anticoagulant effects, including increased bleeding, have been reported when SSRIs or SNRIs are coadministered with warfarin. Patients receiving warfarin therapy should be carefully monitored when sertraline hydrochloride is initiated or discontinued.

Electroconvulsive Therapy

There are no clinical studies establishing the risks or benefits of the combined use of electroconvulsive therapy (ECT) and sertraline hydrochloride.

Alcohol

Although sertraline hydrochloride did not potentiate the cognitive and psychomotor effects of alcohol in experiments with normal subjects, the concomitant use of sertraline hydrochloride and alcohol is not recommended.

Carcinogenesis

Lifetime carcinogenicity studies were carried out in CD-1 mice and Long-Evans rats at doses up to 40 mg/kg/day. These doses correspond to 1 times (mice) and 2 times (rats) the maximum recommended human dose (MRHD) on a mg/m^2 basis. There was a dose-related increase of liver adenomas in male mice receiving sertraline at 10–40 mg/kg (0.25–1.0 times the MRHD on a mg/m^2 basis). No increase was seen in female mice or in rats of either sex receiving the same treatments, nor was there an increase in hepatocellular carcinomas. Liver adenomas have a variable rate of spontaneous occurrence in the CD-1 mouse and are of unknown significance to humans. There was an increase in follicular adenomas of the thyroid in female rats receiving sertraline at 40 mg/kg (2 times the MRHD on a mg/m^2 basis); this was not accompanied by thyroid hyperplasia. While there was an increase in uterine adenocarcinomas in rats receiving sertraline at 10–40 mg/kg (0.5–2.0 times the MRHD on a mg/m^2 basis) compared to placebo controls, this effect was not clearly drug related.

Mutagenesis

Sertraline had no genotoxic effects, with or without metabolic activation, based on the following assays: bacterial mutation assay; mouse lymphoma mutation assay; and tests for cytogenetic aberrations in vivo in mouse bone marrow and in vitro in human lymphocytes.

Impairment of Fertility

A decrease in fertility was seen in one of two rat studies at a dose of 80 mg/kg (4 times the maximum recommended human dose on a mg/m^2 basis).

Pregnancy–Pregnancy Category C

Reproduction studies have been performed in rats and rabbits at doses up to 80 mg/kg/day and 40 mg/kg/day, respectively. These doses correspond to approximately 4 times the maximum recommended human dose (MRHD) on a mg/m^2 basis. There was no evidence of teratogenicity at any dose level. When pregnant rats and rabbits were given sertraline during the period of organogenesis, delayed ossification was observed in fetuses at doses of 10 mg/kg (0.5 times the MRHD on a mg/m^2 basis) in rats and 40 mg/kg (4 times the MRHD on a mg/m^2 basis) in rabbits. When female rats received sertraline during the last third of gestation and throughout lactation, there was an increase in the number of stillborn pups and in the number of pups dying during the first 4 days after birth. Pup body weights were also decreased during the first four days after birth. These effects occurred at a dose of 20 mg/kg (1 times the MRHD on a mg/m^2 basis). The no effect dose for rat pup mortality was 10 mg/kg (0.5 times the MRHD on a mg/m^2 basis). The decrease in pup survival was shown to be due to in utero exposure to sertraline. The clinical significance of these effects is unknown. There are no adequate and well-controlled studies in pregnant women. Sertraline hydrochloride should be used during pregnancy only if the potential benefit justifies the potential risk to the fetus.

Pregnancy-Nonteratogenic Effects

Neonates exposed to sertraline hydrochloride and other SSRIs or SNRIs, late in the third trimester have developed complications requiring prolonged hospitalization, respiratory support, and tube feeding. These findings are based on post marketing reports. Such complications can arise immediately upon delivery. Reported clinical findings have included respiratory distress, cyanosis, apnea, seizures, temperature instability, feeding difficulty, vomiting, hypoglycemia, hypotonia, hypertonia, hyperreflexia, tremor, jitteriness, irritability, and constant crying. These features are consistent with either a direct toxic effect of SSRIs and SNRIs or, possibly, a drug discontinuation syndrome. It should be noted that, in some cases, the clinical picture is consistent with serotonin syndrome (see WARNINGS).

Infants exposed to SSRIs in late pregnancy may have an increased risk for persistent pulmonary hypertension of the newborn (PPHN). PPHN occurs in 1–2 per 1,000 live births in the general population and is associated with substantial neonatal morbidity and mortality. In a retrospective case-control study of 377 women whose infants were born with PPHN and 836 women whose infants were born healthy, the risk for developing PPHN was approximately six-fold higher for infants exposed to SSRIs after the 20th week of gestation compared to infants who had not been exposed to antidepressants during pregnancy. There is currently no corroborative evidence regarding the risk for PPHN following exposure to SSRIs in pregnancy; this is the first study that has investigated the potential risk. The study did not include enough cases with exposure to individual SSRIs to determine if all SSRIs posed similar levels of PPHN risk.

When treating a pregnant woman with sertraline hydrochloride during the third trimester, the physician should carefully consider both the potential risks and benefits of treatment (see DOSAGE AND ADMINISTRATION). Physicians should note that in a prospective longitudinal study of 201 women with a history of major depression who were euthymic in the context of antidepressant therapy at the beginning of pregnancy, women who discontinued antidepressant medication during pregnancy were more likely to experience a relapse of major depression than women who continued antidepressant medication.

Labor and Delivery

The effect of sertraline hydrochloride on labor and delivery in humans is unknown.

Nursing Mothers

It is not known whether, and if so in what amount, sertraline or its metabolites are excreted in human milk. Because many drugs are excreted in human milk, caution should be exercised when sertraline hydrochloride is administered to a nursing woman.

Pediatric Use

The efficacy of sertraline hydrochloride for the treatment of obsessive-compulsive disorder was demonstrated in a 12-week, multicenter, placebo-controlled study with 187 outpatients ages 6–17 (see Clinical Trials under CLINICAL PHARMACOLOGY). Safety and effectiveness in the pediatric population other than pediatric patients with OCD have not been established (see BOX WARNING and WARNINGS-Clinical Worsening and Suicide Risk). Two placebo controlled trials (n=373) in pediatric patients with MDD have been conducted with sertraline hydrochloride, and the data were not sufficient to support a claim for use in pediatric patients. Anyone considering the use of sertraline hydrochloride in a child or adolescent must balance the potential risks with the clinical need.

The safety of sertraline hydrochloride use in children and adolescents with OCD, ages 6–18, was evaluated in a 12-week, multicenter, placebo-controlled study with 187 outpatients, ages 6–17, and in a flexible dose, 52 week open extension study of 137 patients, ages 6–18, who had completed the initial 12-week, double-blind, placebo-controlled study. Sertraline hydrochloride was administered at doses of either 25 mg/day (children, ages 6–12) or 50 mg/day (adolescents, ages 13–18) and then titrated in weekly 25 mg/day or 50 mg/day increments, respectively, to a maximum dose of 200 mg/day based upon clinical response. The mean dose for completers was 157 mg/day. In the acute 12 week pediatric study and in the 52 week study, sertraline hydrochloride had an adverse event profile generally similar to that observed in adults.

Sertraline pharmacokinetics were evaluated in 61 pediatric patients between 6 and 17 years of age with major depressive disorder or OCD and revealed similar drug exposures to those of adults when plasma concentration was adjusted for weight (see Pharmacokinetics under CLINICAL PHARMACOLOGY).

Approximately 600 patients with major depressive disorder or OCD between 6 and 17 years of age have received sertraline hydrochloride in clinical trials, both controlled and uncontrolled. The adverse event profile observed in these patients was generally similar to that observed in adult studies with sertraline hydrochloride (see ADVERSE REACTIONS). As with other SSRIs, decreased appetite and weight loss have been observed in association with the use of sertraline hydrochloride. In a pooled analysis of two 10-week, double-blind, placebo-controlled, flexible dose (50–200 mg) outpatient trials for major depressive disorder (n=373), there was a difference in weight change between sertraline and placebo of roughly 1 kilogram, for both children (ages 6–11) and adolescents (ages 12–17), in both cases representing a slight weight loss for sertraline compared to a slight gain for placebo. At baseline the mean weight for children was 39.0 kg for sertraline and 38.5 kg for placebo. At baseline the mean weight for adolescents was 61.4 kg for sertraline and 62.5 kg for placebo. There was a bigger difference between sertraline and placebo in the proportion of outliers for clinically important weight loss in children than in adolescents. For children, about 7% had a weight loss > 7% of body weight compared to none of the placebo patients; for adolescents, about 2% had a weight loss > 7% of body weight compared to about 1% of the placebo patients. A subset of these patients who completed the randomized controlled trials (sertraline n=99, placebo n=122) were continued into a 24-week, flexible-dose, open-label, extension study. A mean weight loss of approximately 0.5 kg was seen during the first eight weeks of treatment for subjects with first exposure to sertraline during the open-label extension study, similar to mean weight loss observed among sertraline treated subjects during the first eight weeks of the randomized controlled trials. The subjects continuing in the open label study began gaining weight compared to baseline by week 12 of sertraline treatment. Those subjects who completed 34 weeks of sertraline treatment (10 weeks in a placebo controlled trial + 24 weeks open label, n=68) had weight gain that was similar to that expected using data from age-adjusted peers. Regular monitoring of weight and growth is recommended if treatment of a pediatric patient with an SSRI is to be continued long term. Safety and effectiveness in pediatric patients below the age of 6 have not been established.

The risks, if any, that may be associated with sertraline hydrochloride's use beyond 1 year in children and adolescents with OCD or major depressive disorder have not been systematically assessed. The prescriber should be mindful that the evidence relied upon to conclude that sertraline is safe for use in children and adolescents derives from clinical studies that were 10 to 52 weeks in duration and from the extrapolation of experience gained with adult patients. In particular, there are no studies that directly evaluate the effects of long-term sertraline use on the growth, development, and maturation of children and adolescents. Although there is no affirmative finding to suggest that sertraline possesses a capacity to adversely affect growth, development or maturation, the absence of such findings is not compelling evidence of the absence of the potential of sertraline to have adverse effects in chronic use (see WARNINGS – Clinical Worsening and Suicide Risk).

Geriatric Use

U.S. geriatric clinical studies of sertraline hydrochloride in major depressive disorder included 663 sertraline hydrochloride-treated subjects ≥ 65 years of age, of those, 180 were ≥ 75 years of age. No overall differences in the pattern of adverse reactions were observed in the geriatric clinical trial subjects relative to those reported in younger subjects (see ADVERSE REACTIONS), and other reported experience has not identified differences in safety patterns between the elderly and younger subjects. As with all medications, greater sensitivity of some older individuals cannot be ruled out. There were 947 subjects in placebo-controlled geriatric clinical studies of sertraline hydrochloride in major depressive disorder. No overall differences in the pattern of efficacy were observed in the geriatric clinical trial subjects relative to those reported in younger subjects.

Other Adverse Events in Geriatric Patients

In 354 geriatric subjects treated with sertraline hydrochloride in placebo-controlled trials, the overall profile of adverse events was generally similar to that shown in Tables 2 and 3. Urinary tract infection was the only adverse event not appearing in Tables 2 and 3 and reported at an incidence of at least 2% and at a rate greater than placebo in placebo-controlled trials.

SSRIS and SNRIs, including sertraline hydrochloride, have been associated with cases of clinically significant hyponatremia in elderly patients, who may be at greater risk for this adverse event (see PRECAUTIONS, Hyponatremia).

ADVERSE REACTIONS

During its premarketing assessment, multiple doses of sertraline hydrochloride were administered to over 4000 adult subjects as of February 18, 2000. The conditions and duration of exposure to sertraline hydrochloride varied greatly, and included (in overlapping categories) clinical pharmacology studies, open and double-blind studies, uncontrolled and controlled studies, inpatient and outpatient studies, fixed-dose and titration studies, and studies for multiple indications, including major depressive disorder, OCD, panic disorder, PTSD, PMDD and social anxiety disorder.

Untoward events associated with this exposure were recorded by clinical investigators using terminology of their own choosing. Consequently, it is not possible to provide a meaningful estimate of the proportion of individuals experiencing adverse events without first grouping similar types of untoward events into a smaller number of standardized event categories.

In the tabulations that follow, a World Health Organization dictionary of terminology has been used to classify reported adverse events. The frequencies presented, therefore, represent the proportion of the over 4000 adult individuals exposed to multiple doses of sertraline hydrochloride who experienced a treatment-emergent adverse event of the type cited on at least one occasion while receiving sertraline hydrochloride. An event was considered treatment-emergent if it occurred for the first time or worsened while receiving therapy following baseline evaluation. It is important to emphasize that events reported during therapy were not necessarily caused by it.

The prescriber should be aware that the figures in the tables and tabulations cannot be used to predict the incidence of side effects in the course of usual medical practice where patient characteristics and other factors differ from those that prevailed in the clinical trials. Similarly, the cited frequencies cannot be compared with figures obtained from other clinical investigations involving different treatments, uses, and investigators. The cited figures, however, do provide the prescribing physician with some basis for estimating the relative contribution of drug and non-drug factors to the side effect incidence rate in the population studied.

Incidence in Placebo-Controlled Trials

Table 2 enumerates the most common treatment-emergent adverse events associated with the use of sertraline hydrochloride (incidence of at least 5% for sertraline hydrochloride and at least twice that for placebo within at least one of the indications) for the treatment of adult patients with major depressive disorder/other, OCD, panic disorder, PTSD, PMDD and social anxiety disorder in placebo-controlled clinical trials. Most patients in major depressive disorder/other, OCD, panic disorder, PTSD and social anxiety disorder studies received doses of 50 to 200 mg/day. Patients in the PMDD study with daily dosing throughout the menstrual cycle received doses of 50 to 150 mg/day, and in the PMDD study with dosing during the luteal phase of the menstrual cycle received doses of 50 to 100 mg/day. Table 3 enumerates treatment-emergent adverse events that occurred in 2% or more of adult patients treated with sertraline hydrochloride and with incidence greater than placebo who participated in controlled clinical trials comparing sertraline hydrochloride with placebo in the treatment of major depressive disorder/other, OCD, panic disorder, PTSD, PMDD and social anxiety disorder. Table 3 provides combined data for the pool of studies that are provided separately by indication in Table 2.

TABLE 2 MOST COMMON TREATMENT-EMERGENT ADVERSE EVENTS: INCIDENCE IN PLACEBO-CONTROLLED CLINICAL TRIALS
 | Percentage of Patients Reporting Event
 | Major Depressive Disorder/Other |  | OCD |  | Panic Disorder |  | PTSD
Body System/Adverse Event | Sertraline hydrochloride (N=861) | Placebo (N=853) | Sertraline hydrochloride (N=533) | Placebo (N=373) | Sertraline hydrochloride (N=430) | Placebo (N=275) | Sertraline hydrochloride (N=374) | Placebo (N=376)
Autonomic Nervous System Disorders
Ejaculation Failure [Primarily ejaculatory delay. Denominator used was for male patients only (N=271 sertraline hydrochloride major depressive disorder/other*; N=271 placebo major depressive disorder/other*; N=296 sertraline hydrochloride OCD; N=219 placebo OCD; N=216 sertraline hydrochloride panic disorder; N=134 placebo panic disorder; N=130 sertraline hydrochloride PTSD; N=149 placebo PTSD; No male patients in PMDD studies; N=205 sertraline hydrochloride social anxiety disorder; N=153 placebo social anxiety disorder).] | 7 | <1 | 17 | 2 | 19 | 1 | 11 | 1
Mouth Dry | 16 | 9 | 14 | 9 | 15 | 10 | 11 | 6
Sweating Increased | 8 | 3 | 6 | 1 | 5 | 1 | 4 | 2
Center. & Periph. Nerv. System Disorders
Somnolence | 13 | 6 | 15 | 8 | 15 | 9 | 13 | 9
Tremor | 11 | 3 | 8 | 1 | 5 | 1 | 5 | 1
Dizziness | 12 | 7 | 17 | 9 | 10 | 10 | 8 | 5
General
Fatigue | 11 | 8 | 14 | 10 | 11 | 6 | 10 | 5
Pain | 1 | 2 | 3 | 1 | 3 | 3 | 4 | 6
Malaise | <1 | 1 | 1 | 1 | 7 | 14 | 10 | 10
Gastrointestinal Disorders
Abdominal Pain | 2 | 2 | 5 | 5 | 6 | 7 | 6 | 5
Anorexia | 3 | 2 | 11 | 2 | 7 | 2 | 8 | 2
Constipation | 8 | 6 | 6 | 4 | 7 | 3 | 3 | 3
Diarrhea/Loose Stools | 18 | 9 | 24 | 10 | 20 | 9 | 24 | 15
Dyspepsia | 6 | 3 | 10 | 4 | 10 | 8 | 6 | 6
Nausea | 26 | 12 | 30 | 11 | 29 | 18 | 21 | 11
Psychiatric Disorders
Agitation | 6 | 4 | 6 | 3 | 6 | 2 | 5 | 5
Insomnia | 16 | 9 | 28 | 12 | 25 | 18 | 20 | 11
Libido Decreased | 1 | <1 | 11 | 2 | 7 | 1 | 7 | 2
 | PMDD Daily Dosing |  | PMDD Luteal Phase Dosing |  | Social Anxiety Disorder
Body System/Adverse Event | Sertraline hydrochloride (N=121) | Placebo (N=122) | Sertraline hydrochloride (N=136) | Placebo (N=127) | Sertraline hydrochloride (N=344) | Placebo (N=268)
Autonomic Nervous System Disorders
Ejaculation Failure | N/A | N/A | N/A | N/A | 14 | -
Mouth Dry | 6 | 3 | 10 | 3 | 12 | 4
Sweating Increased | 6 | <1 | 3 | 0 | 11 | 2
Center. & Periph. Nerv. System Disorders
Somnolence | 7 | <1 | 2 | 0 | 9 | 6
Tremor | 2 | 0 | <1 | <1 | 9 | 3
Dizziness | 6 | 3 | 7 | 5 | 14 | 6
General
Fatigue | 16 | 7 | 10 | <1 | 12 | 6
Pain | 6 | <1 | 3 | 2 | 1 | 3
Malaise | 9 | 5 | 7 | 5 | 8 | 3
Gastrointestinal Disorders
Abdominal Pain | 7 | <1 | 3 | 3 | 5 | 5
Anorexia | 3 | 2 | 5 | 0 | 6 | 3
Constipation | 2 | 3 | 1 | 2 | 5 | 3
Diarrhea/Loose Stools | 13 | 3 | 13 | 7 | 21 | 8
Dyspepsia | 7 | 2 | 7 | 3 | 13 | 5
Nausea | 23 | 9 | 13 | 3 | 22 | 8
Psychiatric Disorders
Agitation | 2 | <1 | 1 | 0 | 4 | 2
Insomnia | 17 | 11 | 12 | 10 | 25 | 10
Libido Decreased | 11 | 2 | 4 | 2 | 9 | 3

TABLE 3 TREATMENT-EMERGENT ADVERSE EVENTS: INCIDENCE IN PLACEBO-CONTROLLED CLINICAL TRIALS Percentage of Patients Reporting Event Major Depressive Disorder/Other, OCD, Panic Disorder, PTSD, PMDD and Social Anxiety Disorder combined
Body System/Adverse Event | SERTRALINE HYDROCHLORIDE (N=2799) | Placebo (N=2394)
Autonomic Nervous System Disorders
Ejaculation Failure | 14 | 1
Mouth Dry | 14 | 8
Sweating Increased | 7 | 2
Center. & Periph. Nerv. System Disorders
Somnolence | 13 | 7
Dizziness | 12 | 7
Headache | 25 | 23
Paresthesia | 2 | 1
Tremor | 8 | 2
Disorders of Skin and Appendages
Rash | 3 | 2
Gastrointestinal Disorders
Anorexia | 6 | 2
Constipation | 6 | 4
Diarrhea/Loose Stools | 20 | 10
Dyspepsia | 8 | 4
Nausea | 25 | 11
Vomiting | 4 | 2
General
Fatigue | 12 | 7
Psychiatric Disorders
Agitation | 5 | 3
Anxiety | 4 | 3
Insomnia | 21 | 11
Libido Decreased | 6 | 2
Nervousness | 5 | 4
Special Senses
Vision Abnormal | 3 | 2

Associated with Discontinuation in Placebo-Controlled Clinical Trials

Table 4 lists the adverse events associated with discontinuation of sertraline hydrochloride treatment (incidence at least twice that for placebo and at least 1% for sertraline hydrochloride in clinical trials) in major depressive disorder/other, OCD, panic disorder, PTSD, PMDD and social anxiety disorder.

TABLE 4 MOST COMMON ADVERSE EVENTS ASSOCIATED WITH DISCONTINUATION IN PLACEBO-CONTROLLED CLINICAL TRIALS
Adverse Event | Major Depressive Disorder/Other [Major depressive disorder and other premarketing controlled trials.] , OCD, Panic Disorder, PTSD, PMDD and Social Anxiety Disorder combined (N=2799) | Major Depressive Disorder/ Other (N=861) | OCD (N=533) | Panic Disorder (N=430) | PTSD (N=374) | PMDD Daily Dosing (N=121) | PMDD Luteal Phase Dosing (N=136) | Social Anxiety Disorder (N=344)
Abdominal Pain | – | – | – | – | – | – | – | 1%
Agitation | – | 1% | – | 2% | – | – | – | –
Anxiety | – | – | – | – | – | – | – | 2%
Diarrhea/ Loose Stools | 2% | 2% | 2% | 1% | – | 2% | – | –
Dizziness | – | – | 1% | – | – | – | – | –
Dry Mouth | – | 1% | – | – | – | – | – | –
Dyspepsia | – | – | – | 1% | – | – | – | –
Ejaculation Failure | 1% | 1% | 1% | 2% | – | N/A | N/A | 2%
Fatigue | – | – | – | – | – | – | – | 2%
Headache | 1% | 2% | – | – | 1% | – | – | 2%
Hot Flushes | – | – | – | – | – | – | 1% | –
Insomnia | 2% | 1% | 3% | 2% | – | – | 1% | 3%
Nausea | 3% | 4% | 3% | 3% | 2% | 2% | 1% | 2%
Nervousness | – | – | – | – | – | 2% | – | –
Palpitation | – | – | – | – | – | – | 1% | –
Somnolence | 1% | 1% | 2% | 2% | – | – | – | –
Tremor | – | 2% | – | – | – | – | – | –

Male and Female Sexual Dysfunction with SSRIs

Although changes in sexual desire, sexual performance and sexual satisfaction often occur as manifestations of a psychiatric disorder, they may also be a consequence of pharmacologic treatment. In particular, some evidence suggests that selective serotonin reuptake inhibitors (SSRIs) can cause such untoward sexual experiences. Reliable estimates of the incidence and severity of untoward experiences involving sexual desire, performance and satisfaction are difficult to obtain, however, in part because patients and physicians may be reluctant to discuss them. Accordingly, estimates of the incidence of untoward sexual experience and performance cited in product labeling are likely to underestimate their actual incidence.

Table 5 below displays the incidence of sexual side effects reported by at least 2% of patients taking sertraline hydrochloride in placebo-controlled trials.

TABLE 5
Adverse Event | Sertraline hydrochloride | Placebo
Ejaculation failure (primarily delayed ejaculation) | 14% | 1%
Decreased libido | 6% | 1%

There are no adequate and well-controlled studies examining sexual dysfunction with sertraline treatment.

Priapism has been reported with all SSRIs.

While it is difficult to know the precise risk of sexual dysfunction associated with the use of SSRIs, physicians should routinely inquire about such possible side effects.

Other Adverse Events in Pediatric Patients

In over 600 pediatric patients treated with sertraline hydrochloride, the overall profile of adverse events was generally similar to that seen in adult studies. However, the following adverse events, from controlled trials, not appearing in Tables 2 and 3, were reported at an incidence of at least 2% and occurred at a rate of at least twice the placebo rate (N=281 patients treated with sertraline hydrochloride): fever, hyperkinesia, urinary incontinence, aggressive reaction, sinusitis, epistaxis and purpura.

Other Events Observed During the Premarketing Evaluation of sertraline hydrochloride

Following is a list of treatment-emergent adverse events reported during premarketing assessment of sertraline hydrochloride in clinical trials (over 4000 adult subjects) except those already listed in the previous tables or elsewhere in labeling.

In the tabulations that follow, a World Health Organization dictionary of terminology has been used to classify reported adverse events. The frequencies presented, therefore, represent the proportion of the over 4000 adult individuals exposed to multiple doses of sertraline hydrochloride who experienced an event of the type cited on at least one occasion while receiving sertraline hydrochloride. All events are included except those already listed in the previous tables or elsewhere in labeling and those reported in terms so general as to be uninformative and those for which a causal relationship to sertraline hydrochloride treatment seemed remote. It is important to emphasize that although the events reported occurred during treatment with sertraline hydrochloride, they were not necessarily caused by it.

Events are further categorized by body system and listed in order of decreasing frequency according to the following definitions: frequent adverse events are those occurring on one or more occasions in at least 1/100 patients; infrequent adverse events are those occurring in 1/100 to 1/1000 patients; rare events are those occurring in fewer than 1/1000 patients. Events of major clinical importance are also described in the PRECAUTIONS section.

Autonomic Nervous System Disorders–Frequent: impotence; Infrequent: flushing, increased saliva, cold clammy skin, mydriasis; Rare: pallor, glaucoma, priapism, vasodilation.

Body as a Whole–General Disorders–Rare: allergic reaction, allergy.

Cardiovascular–Frequent: palpitations, chest pain; Infrequent: hypertension, tachycardia, postural dizziness, postural hypotension, periorbital edema, peripheral edema, hypotension, peripheral ischemia, syncope, edema, dependent edema; Rare: precordial chest pain, substernal chest pain, aggravated hypertension, myocardial infarction, cerebrovascular disorder.

Central and Peripheral Nervous System Disorders–Frequent: hypertonia, hypoesthesia; Infrequent: twitching, confusion, hyperkinesia, vertigo, ataxia, migraine, abnormal coordination, hyperesthesia, leg cramps, abnormal gait, nystagmus, hypokinesia; Rare: dysphonia, coma, dyskinesia, hypotonia, ptosis, choreoathetosis, hyporeflexia.

Disorders of Skin and Appendages–Infrequent: pruritus, acne, urticaria, alopecia, dry skin, erythematous rash, photosensitivity reaction, maculopapular rash; Rare: follicular rash, eczema, dermatitis, contact dermatitis, bullous eruption, hypertrichosis, skin discoloration, pustular rash.

Endocrine Disorders–Rare: exophthalmos, gynecomastia.

Gastrointestinal Disorders–Frequent: appetite increased; Infrequent: dysphagia, tooth caries aggravated, eructation, esophagitis, gastroenteritis; Rare: melena, glossitis, gum hyperplasia, hiccup, stomatitis, tenesmus, colitis, diverticulitis, fecal incontinence, gastritis, rectum hemorrhage, hemorrhagic peptic ulcer, proctitis, ulcerative stomatitis, tongue edema, tongue ulceration.

General–Frequent: back pain, asthenia, malaise, weight increase; Infrequent: fever, rigors, generalized edema; Rare: face edema, aphthous stomatitis.

Hearing and Vestibular Disorders–Rare: hyperacusis, labyrinthine disorder.

Hematopoietic and Lymphatic–Rare: anemia, anterior chamber eye hemorrhage.

Liver and Biliary System Disorders–Rare: abnormal hepatic function.

Metabolic and Nutritional Disorders–Infrequent: thirst; Rare: hypoglycemia, hypoglycemia reaction.

Musculoskeletal System Disorders–Frequent: myalgia; Infrequent: arthralgia, dystonia, arthrosis, muscle cramps, muscle weakness.

Psychiatric Disorders–Frequent: yawning, other male sexual dysfunction, other female sexual dysfunction; Infrequent: depression, amnesia, paroniria, teeth-grinding, emotional lability, apathy, abnormal dreams, euphoria, paranoid reaction, hallucination, aggressive reaction, aggravated depression, delusions; Rare: withdrawal syndrome, suicide ideation, libido increased, somnambulism, illusion.

Reproductive–Infrequent: menstrual disorder, dysmenorrhea, intermenstrual bleeding, vaginal hemorrhage, amenorrhea, leukorrhea; Rare: female breast pain, menorrhagia, balanoposthitis, breast enlargement, atrophic vaginitis, acute female mastitis.

Respiratory System Disorders–Frequent: rhinitis; Infrequent: coughing, dyspnea, upper respiratory tract infection, epistaxis, bronchospasm, sinusitis; Rare: hyperventilation, bradypnea, stridor, apnea, bronchitis, hemoptysis, hypoventilation, laryngismus, laryngitis.

Special Senses–Frequent: tinnitus; Infrequent: conjunctivitis, earache, eye pain, abnormal accommodation; Rare: xerophthalmia, photophobia, diplopia, abnormal lacrimation, scotoma, visual field defect.

Urinary System Disorders–Infrequent: micturition frequency, polyuria, urinary retention, dysuria, nocturia, urinary incontinence; Rare: cystitis, oliguria, pyelonephritis, hematuria, renal pain, strangury.

Laboratory Tests

In man, asymptomatic elevations in serum transaminases (SGOT [or AST] and SGPT [or ALT]) have been reported infrequently (approximately 0.8%) in association with sertraline hydrochloride administration. These hepatic enzyme elevations usually occurred within the first 1 to 9 weeks of drug treatment and promptly diminished upon drug discontinuation.

Sertraline hydrochloride therapy was associated with small mean increases in total cholesterol (approximately 3%) and triglycerides (approximately 5%), and a small mean decrease in serum uric acid (approximately 7%) of no apparent clinical importance.

The safety profile observed with sertraline hydrochloride treatment in patients with major depressive disorder, OCD, panic disorder, PTSD, PMDD and social anxiety disorder is similar.

Other Events Observed During the Post marketing Evaluation of sertraline hydrochloride

Reports of adverse events temporally associated with sertraline hydrochloride that have been received since market introduction, that are not listed above and that may have no causal relationship with the drug, include the following: acute renal failure, anaphylactoid reaction, angioedema, blindness, optic neuritis, cataract, increased coagulation times, bradycardia, AV block, atrial arrhythmias, QT-interval prolongation, ventricular tachycardia (including torsade de pointes-type arrhythmias), hypothyroidism, agranulocytosis, aplastic anemia and pancytopenia, leukopenia, thrombocytopenia, lupus-like syndrome, serum sickness, hyperglycemia, galactorrhea, hyperprolactinemia, extrapyramidal symptoms, oculogyric crisis, serotonin syndrome, psychosis, pulmonary hypertension, severe skin reactions, which potentially can be fatal, such as Stevens-Johnson syndrome, vasculitis, photosensitivity and other severe cutaneous disorders, rare reports of pancreatitis, and liver events—clinical features (which in the majority of cases appeared to be reversible with discontinuation of sertraline hydrochloride) occurring in one or more patients include: elevated enzymes, increased bilirubin, hepatomegaly, hepatitis, jaundice, abdominal pain, vomiting, liver failure and death.

DRUG ABUSE AND DEPENDENCE

Controlled Substance Class

Sertraline hydrochloride is not a controlled substance.

Physical and Psychological Dependence

In a placebo-controlled, double-blind, randomized study of the comparative abuse liability of sertraline hydrochloride, alprazolam, and d-amphetamine in humans, sertraline hydrochloride did not produce the positive subjective effects indicative of abuse potential, such as euphoria or drug liking, that were observed with the other two drugs. Premarketing clinical experience with sertraline hydrochloride did not reveal any tendency for a withdrawal syndrome or any drug-seeking behavior. In animal studies sertraline hydrochloride does not demonstrate stimulant or barbiturate-like (depressant) abuse potential. As with any CNS active drug, however, physicians should carefully evaluate patients for history of drug abuse and follow such patients closely, observing them for signs of sertraline hydrochloride misuse or abuse (e.g., development of tolerance, incrementation of dose, drug-seeking behavior).

OVERDOSAGE

Human Experience

Of 1,027 cases of overdose involving sertraline hydrochloride worldwide, alone or with other drugs, there were 72 deaths (circa 1999).

Among 634 overdoses in which sertraline hydrochloride was the only drug ingested, 8 resulted in fatal outcome, 75 completely recovered, and 27 patients experienced sequelae after overdosage to include alopecia, decreased libido, diarrhea, ejaculation disorder, fatigue, insomnia, somnolence and serotonin syndrome. The remaining 524 cases had an unknown outcome. The most common signs and symptoms associated with non-fatal sertraline hydrochloride overdosage were somnolence, vomiting, tachycardia, nausea, dizziness, agitation and tremor.

The largest known ingestion was 13.5 grams in a patient who took sertraline hydrochloride alone and subsequently recovered. However, another patient who took 2.5 grams of sertraline hydrochloride alone experienced a fatal outcome.

Other important adverse events reported with sertraline hydrochloride overdose (single or multiple drugs) include bradycardia, bundle branch block, coma, convulsions, delirium, hallucinations, hypertension, hypotension, manic reaction, pancreatitis, QT-interval prolongation, serotonin syndrome, stupor and syncope.

Overdose Management

Treatment should consist of those general measures employed in the management of overdosage with any antidepressant.

Ensure an adequate airway, oxygenation and ventilation. Monitor cardiac rhythm and vital signs. General supportive and symptomatic measures are also recommended. Induction of emesis is not recommended. Gastric lavage with a large-bore orogastric tube with appropriate airway protection, if needed, may be indicated if performed soon after ingestion, or in symptomatic patients.

Activated charcoal should be administered. Due to large volume of distribution of this drug, forced diuresis, dialysis, hemoperfusion and exchange transfusion are unlikely to be of benefit. No specific antidotes for sertraline are known.

In managing overdosage, consider the possibility of multiple drug involvement. The physician should consider contacting a poison control center on the treatment of any overdose. Telephone numbers for certified poison control centers are listed in the Physicians' Desk Reference® (PDR®).

DOSAGE AND ADMINISTRATION

Initial Treatment

Dosage for Adults

Major Depressive Disorder and Obsessive-Compulsive Disorder

Sertraline hydrochloride treatment should be administered at a dose of 50 mg once daily.

Panic Disorder, Posttraumatic Stress Disorder and Social Anxiety Disorder

Sertraline hydrochloride treatment should be initiated with a dose of 25 mg once daily. After one week, the dose should be increased to 50 mg once daily.

While a relationship between dose and effect has not been established for major depressive disorder, OCD, panic disorder, PTSD or social anxiety disorder, patients were dosed in a range of 50–200 mg/day in the clinical trials demonstrating the effectiveness of sertraline hydrochloride for the treatment of these indications. Consequently, a dose of 50 mg, administered once daily, is recommended as the initial therapeutic dose. Patients not responding to a 50 mg dose may benefit from dose increases up to a maximum of 200 mg/day. Given the 24 hour elimination half-life of sertraline hydrochloride, dose changes should not occur at intervals of less than 1 week.

Premenstrual Dysphoric Disorder

Sertraline hydrochloride treatment should be initiated with a dose of 50 mg/day, either daily throughout the menstrual cycle or limited to the luteal phase of the menstrual cycle, depending on physician assessment.

While a relationship between dose and effect has not been established for PMDD, patients were dosed in the range of 50–150 mg/day with dose increases at the onset of each new menstrual cycle (see Clinical Trials under CLINICAL PHARMACOLOGY). Patients not responding to a 50 mg/day dose may benefit from dose increases (at 50 mg increments/menstrual cycle) up to 150 mg/day when dosing daily throughout the menstrual cycle, or 100 mg/day when dosing during the luteal phase of the menstrual cycle. If a 100 mg/day dose has been established with luteal phase dosing, a 50 mg/day titration step for three days should be utilized at the beginning of each luteal phase dosing period.

Sertraline hydrochloride should be administered once daily, either in the morning or evening.

Dosage for Pediatric Population (Children and Adolescents)

Obsessive-Compulsive Disorder

Sertraline hydrochloride treatment should be initiated with a dose of 25 mg once daily in children (ages 6–12) and at a dose of 50 mg once daily in adolescents (ages 13–17).

While a relationship between dose and effect has not been established for OCD, patients were dosed in a range of 25–200 mg/day in the clinical trials demonstrating the effectiveness of sertraline hydrochloride for pediatric patients (6–17 years) with OCD. Patients not responding to an initial dose of 25 or 50 mg/day may benefit from dose increases up to a maximum of 200 mg/day. For children with OCD, their generally lower body weights compared to adults should be taken into consideration in advancing the dose, in order to avoid excess dosing. Given the 24 hour elimination half-life of sertraline hydrochloride, dose changes should not occur at intervals of less than 1 week.

Sertraline hydrochloride should be administered once daily, either in the morning or evening.

Maintenance/Continuation/Extended Treatment

Major Depressive Disorder

It is generally agreed that acute episodes of major depressive disorder require several months or longer of sustained pharmacologic therapy beyond response to the acute episode. Systematic evaluation of sertraline hydrochloride has demonstrated that its antidepressant efficacy is maintained for periods of up to 44 weeks following 8 weeks of initial treatment at a dose of 50–200 mg/day (mean dose of 70 mg/day) (see Clinical Trials under CLINICAL PHARMACOLOGY). It is not known whether the dose of sertraline hydrochloride needed for maintenance treatment is identical to the dose needed to achieve an initial response. Patients should be periodically reassessed to determine the need for maintenance treatment.

Posttraumatic Stress Disorder

It is generally agreed that PTSD requires several months or longer of sustained pharmacological therapy beyond response to initial treatment. Systematic evaluation of sertraline hydrochloride has demonstrated that its efficacy in PTSD is maintained for periods of up to 28 weeks following 24 weeks of treatment at a dose of 50–200 mg/day (see Clinical Trials under CLINICAL PHARMACOLOGY). It is not known whether the dose of sertraline hydrochloride needed for maintenance treatment is identical to the dose needed to achieve an initial response. Patients should be periodically reassessed to determine the need for maintenance treatment.

Social anxiety disorder is a chronic condition that may require several months or longer of sustained pharmacological therapy beyond response to initial treatment. Systematic evaluation of sertraline hydrochloride has demonstrated that its efficacy in social anxiety disorder is maintained for periods of up to 24 weeks following 20 weeks of treatment at a dose of 50–200 mg/day (see Clinical Trials under CLINICAL PHARMACOLOGY). Dosage adjustments should be made to maintain patients on the lowest effective dose and patients should be periodically reassessed to determine the need for long-term treatment.

Obsessive-Compulsive Disorder and Panic Disorder

It is generally agreed that OCD and Panic Disorder require several months or longer of sustained pharmacological therapy beyond response to initial treatment. Systematic evaluation of continuing sertraline hydrochloride for periods of up to 28 weeks in patients with OCD and Panic Disorder who have responded while taking sertraline hydrochloride during initial treatment phases of 24 to 52 weeks of treatment at a dose range of 50–200 mg/day has demonstrated a benefit of such maintenance treatment (see Clinical Trials under CLINICAL PHARMACOLOGY). It is not known whether the dose of sertraline hydrochloride needed for maintenance treatment is identical to the dose needed to achieve an initial response. Nevertheless, patients should be periodically reassessed to determine the need for maintenance treatment.

Premenstrual Dysphoric Disorder

The effectiveness of sertraline hydrochloride in long-term use, that is, for more than 3 menstrual cycles, has not been systematically evaluated in controlled trials. However, as women commonly report that symptoms worsen with age until relieved by the onset of menopause, it is reasonable to consider continuation of a responding patient. Dosage adjustments, which may include changes between dosage regimens (e.g., daily throughout the menstrual cycle versus during the luteal phase of the menstrual cycle), may be needed to maintain the patient on the lowest effective dosage and patients should be periodically reassessed to determine the need for continued treatment.

Switching Patients to or from a Monoamine Oxidase Inhibitor

At least 14 days should elapse between discontinuation of an MAOI and initiation of therapy with sertraline hydrochloride. In addition, at least 14 days should be allowed after stopping sertraline hydrochloride before starting an MAOI (see CONTRAINDICATIONS and WARNINGS).

Special Populations

Dosage for Hepatically Impaired Patients

The use of sertraline in patients with liver disease should be approached with caution. The effects of sertraline in patients with moderate and severe hepatic impairment have not been studied. If sertraline is administered to patients with liver impairment, a lower or less frequent dose should be used (see CLINICAL PHARMACOLOGY and PRECAUTIONS).

Treatment of Pregnant Women During the Third Trimester

Neonates exposed to sertraline hydrochloride and other SSRIs or SNRIs, late in the third trimester have developed complications requiring prolonged hospitalization, respiratory support, and tube feeding (see PRECAUTIONS). When treating pregnant women with sertraline hydrochloride during the third trimester, the physician should carefully consider the potential risks and benefits of treatment. The physician may consider tapering sertraline hydrochloride in the third trimester.

Discontinuation of Treatment with sertraline hydrochloride

Symptoms associated with discontinuation of sertraline hydrochloride and other SSRIs and SNRIs, have been reported (see PRECAUTIONS). Patients should be monitored for these symptoms when discontinuing treatment. A gradual reduction in the dose rather than abrupt cessation is recommended whenever possible. If intolerable symptoms occur following a decrease in the dose or upon discontinuation of treatment, then resuming the previously prescribed dose may be considered. Subsequently, the physician may continue decreasing the dose but at a more gradual rate.

Sertraline hydrochloride Oral Concentrate contains 20 mg/mL of sertraline (as the hydrochloride) as the active ingredient and 12% alcohol. Sertraline hydrochloride Oral Concentrate must be diluted before use. Just before taking, use the dropper provided to remove the required amount of sertraline hydrochloride Oral Concentrate and mix with 4 oz (1/2 cup) of water, ginger ale, lemon/lime soda, lemonade or orange juice ONLY. Do not mix sertraline hydrochloride Oral Concentrate with anything other than the liquids listed. The dose should be taken immediately after mixing. Do not mix in advance. At times, a slight haze may appear after mixing; this is normal. Note that caution should be exercised for patients with latex sensitivity, as the dropper dispenser contains dry natural rubber.

Sertraline hydrochloride Oral Concentrate is contraindicated with ANTABUSE (disulfiram) due to the alcohol content of the concentrate.

HOW SUPPLIED

Sertraline hydrochloride capsular-shaped scored tablets, equivalent to 25, 50 and 100 mg of sertraline, are packaged in bottles.

Sertraline hydrochloride 25 mg Tablets: light green capsular-shaped scored tablets engraved on one side with G 4960 and on the other side engraved with 25 mg.

NDC 59762-4960-1 Bottles of 30

Sertraline hydrochloride 50 mg Tablets: light blue capsular-shaped scored tablets engraved on one side with G 4900 and on the other side engraved with 50 mg.

NDC 59762-4900-1 Bottles of 30
NDC 59762-4900-4 Bottles of 100
NDC 59762-4900-5 Bottles of 500
NDC 59762-4900-2 Bottles of 5000
NDC 59762-4900-3 Unit Dose Packages of 100

Sertraline hydrochloride 100 mg Tablets: light yellow capsular-shaped scored tablets engraved on one side with G 4910 and on the side engraved with 100 mg.

NDC 59762-4910-1 Bottles of 30
NDC 59762-4910-4 Bottles of 100
NDC 59762-4910-5 Bottles of 500
NDC 59762-4910-2 Bottles of 5000
NDC 59762-4910-3 Unit Dose Packages of 100

Store at 25°C (77°F); excursions permitted to 15° – 30°C (59° – 86°F)[see USP Controlled Room Temperature].

Sertraline hydrochloride Oral Concentrate: sertraline hydrochloride Oral Concentrate is a clear, colorless solution with a menthol scent containing sertraline hydrochloride equivalent to 20 mg of sertraline per mL and 12% alcohol. It is supplied as a 60 mL bottle with an accompanying calibrated dropper.

NDC 59762-4940-1 Bottles of 60 mL

Store at 25°C (77°F); excursions permitted to 15° – 30°C (59° – 86°F) [see USP Controlled Room Temperature].

Rx only

LAB—0340—12.0

January 2009

Medication Guide Antidepressant Medicines, Depression and other Serious Mental Illness, and Suicidal Thoughts or Actions

Read the Medication Guide that comes with you or your family member's antidepressant medicine. This Medication Guide is only about the risk of suicidal thoughts and actions with antidepressant medicines. Talk to your, or your family member's healthcare provider about:

- all risks and benefits of treatment with antidepressant medicines
- all treatment choices for depression or other serious mental illness

What is the most important information I should know about antidepressant medicines, depression, and other serious mental illnesses, and suicidal thoughts or actions?

- 1. Antidepressant medicines may increase suicidal thoughts or actions in some children, teenagers, and young adults within the first few months of treatment.
- 2. Depression and other serious mental illnesses are the most important causes of suicidal thoughts and actions. Some people may have a particularly high risk of having suicidal thoughts or actions. These include people who have (or have a family history of) bipolar illness (also called manic-depressive illness) or suicidal thoughts or actions.
- 3. How can I watch for and try to prevent suicidal thoughts and actions in myself or a family member?

Call a healthcare provider right away if you or your family member has any of the following symptoms especially if they are new, worse, or worry you:

- thoughts about suicide or dying
- attempts to commit suicide
- new or worse depression
- new or worse anxiety
- feeling very agitated or restless
- panic attacks
- trouble sleeping (insomnia)
- new or worse irritability
- acting aggressive, being angry, or violent
- acting on dangerous impulses
- an extreme increase in activity and talking (mania)
- other unusual changes in behavior or mood

Call your doctor for medical advice about side effects. You may report side effects to FDA at 1-800-FDA-1088

What else do I need to know about antidepressant medicines?

- Never stop an antidepressant medicine without first talking to a healthcare provider. Stopping an antidepressant medicine suddenly can cause other symptoms.
- Antidepressants are medicines used to treat depression and other illnesses. It is important to discuss all the risks of treating depression and also the risks of not treating it. Patients and their families or other caregivers should discuss all treatment choices with the healthcare provider, not just the use of antidepressants.
- Antidepressant medicines have other side effects. Talk to the healthcare provider about the side effects of the medicine prescribed for you or your family member.
- Antidepressant medicines can interact with other medicines. Know all of the medicines that you or your family member takes. Keep a list of all medicines to show the healthcare provider. Do not start new medicines without first checking with your healthcare provider.
- Not all antidepressant medicines prescribed for children are FDA approved for use in children. Talk with your child's healthcare provider for more information.

This Medication Guide has been approved by the U.S. Food and Drug Administration for all antidepressants.

October 2008